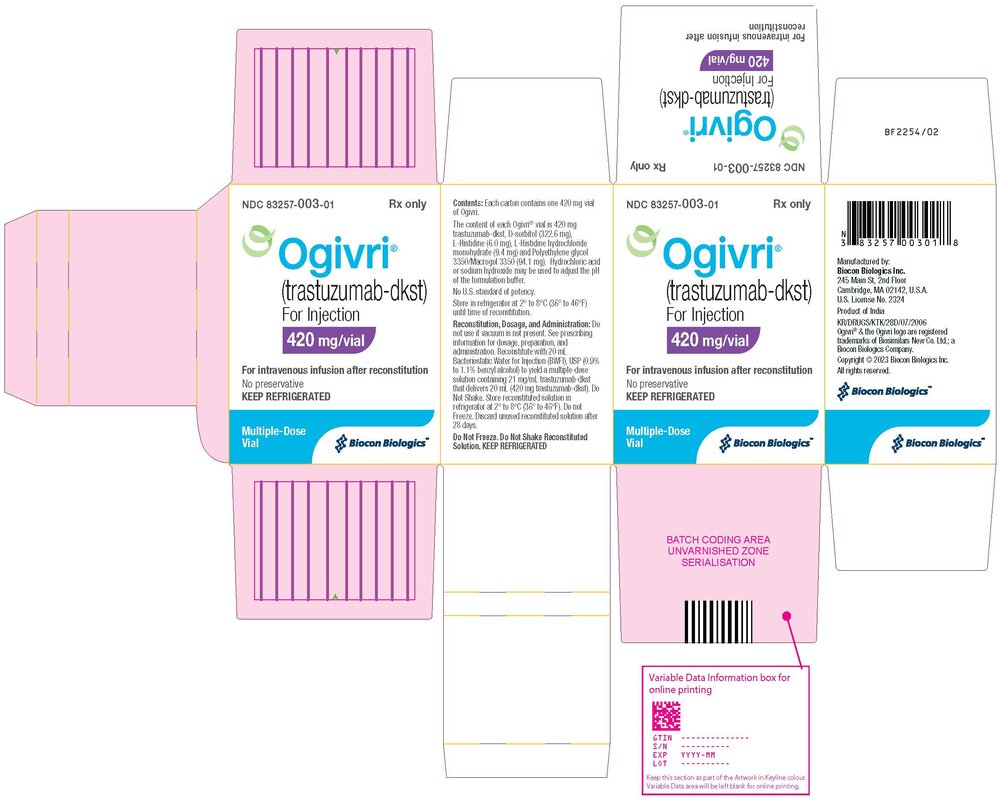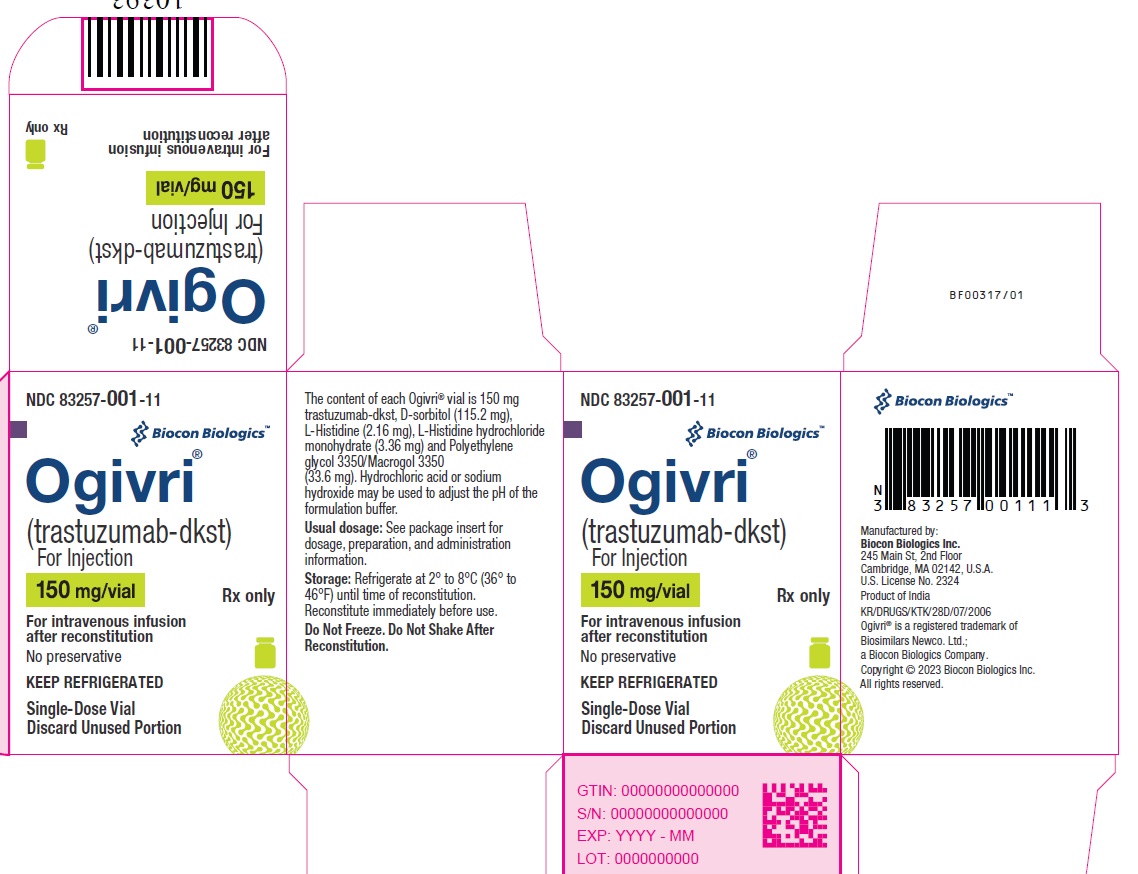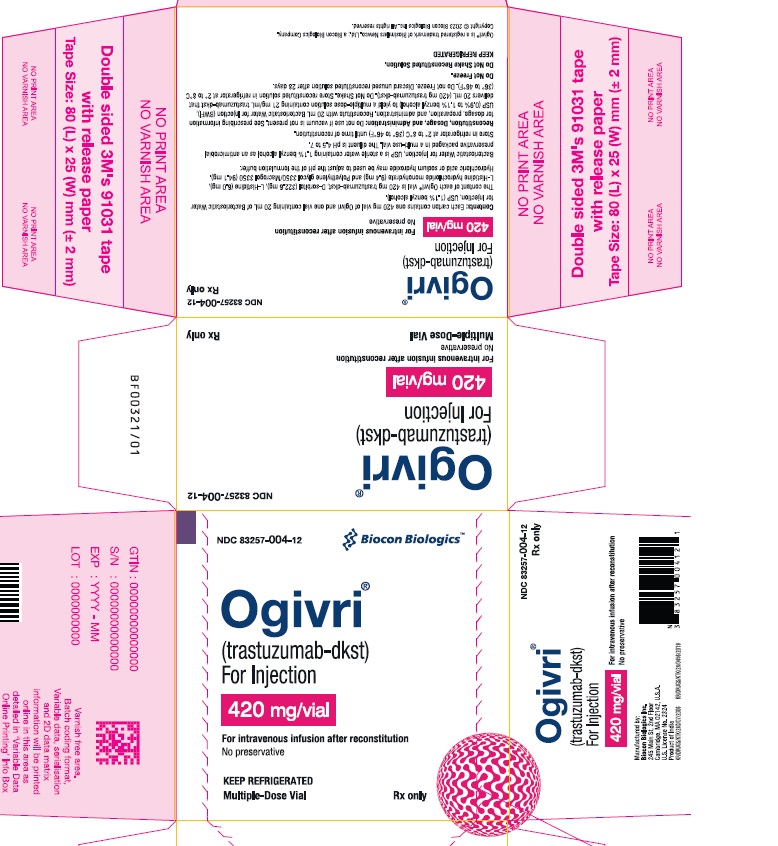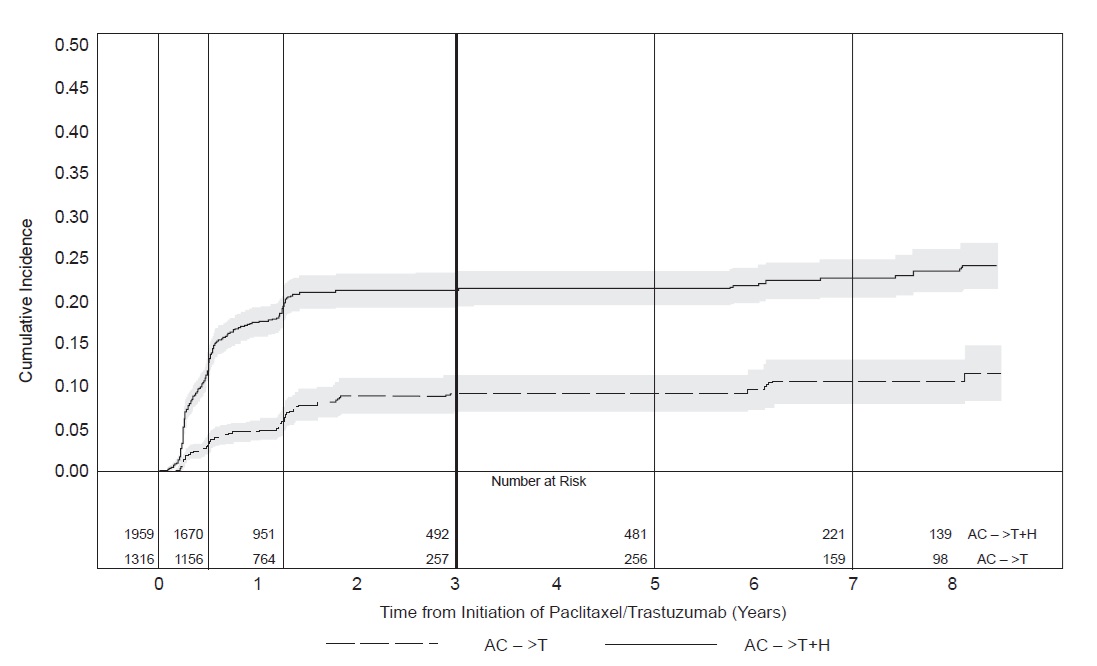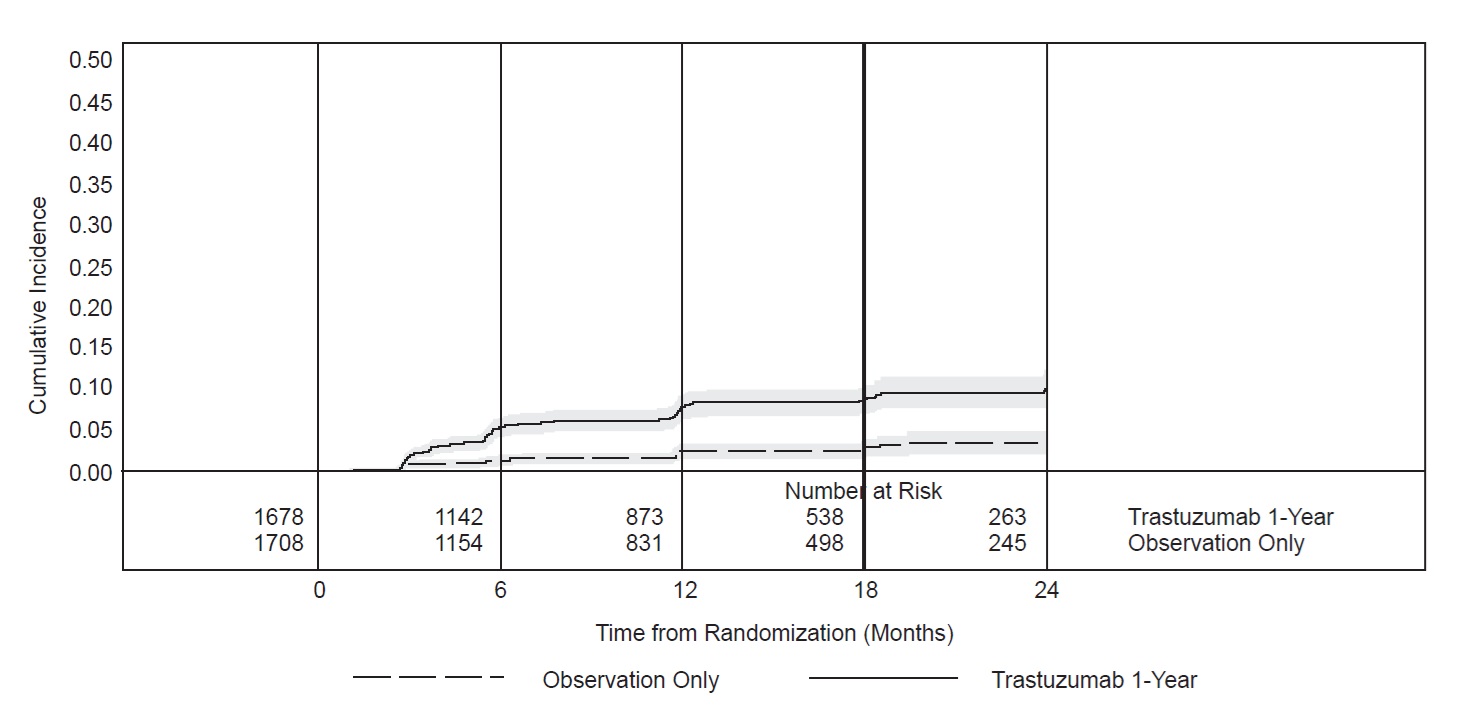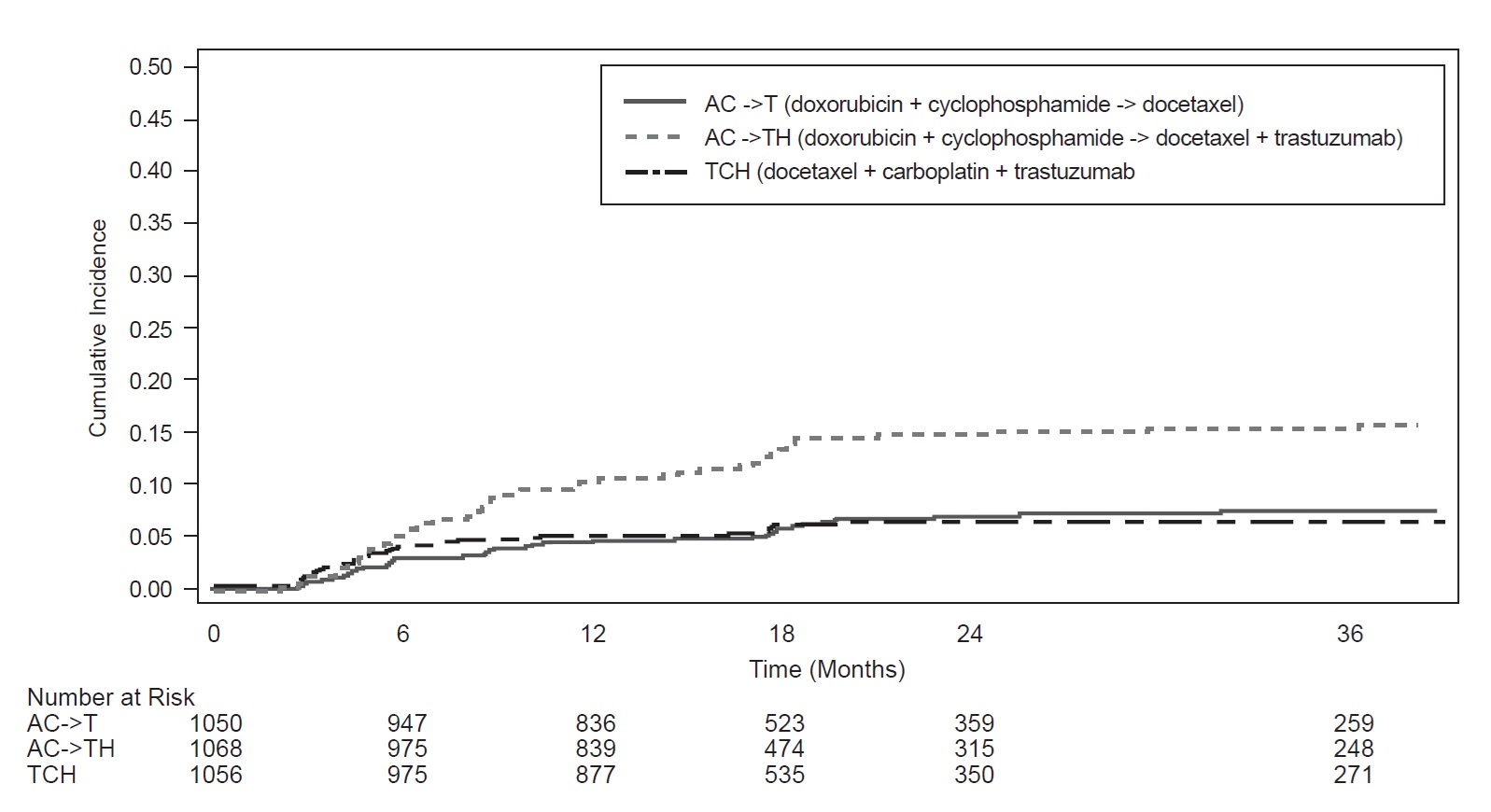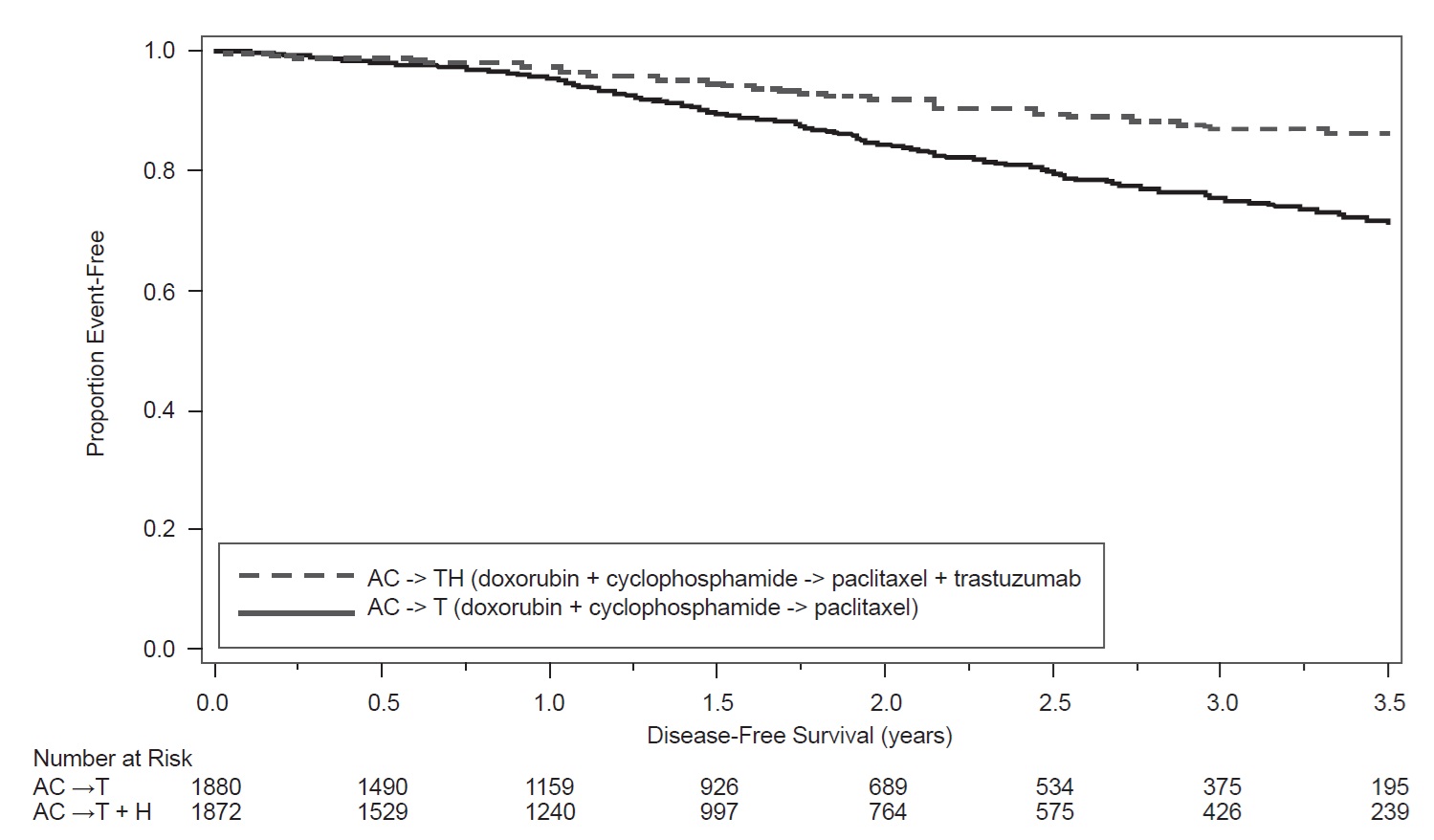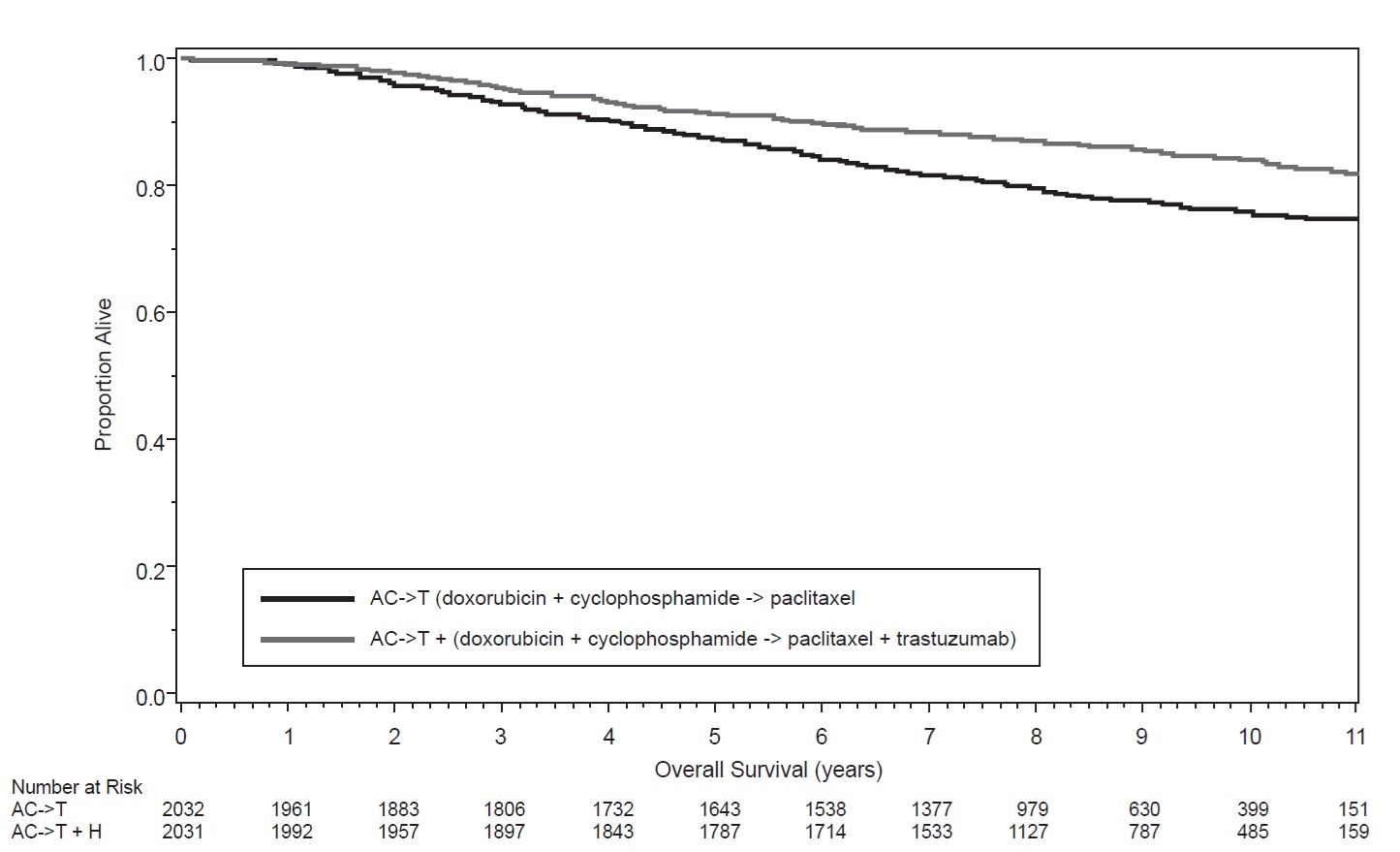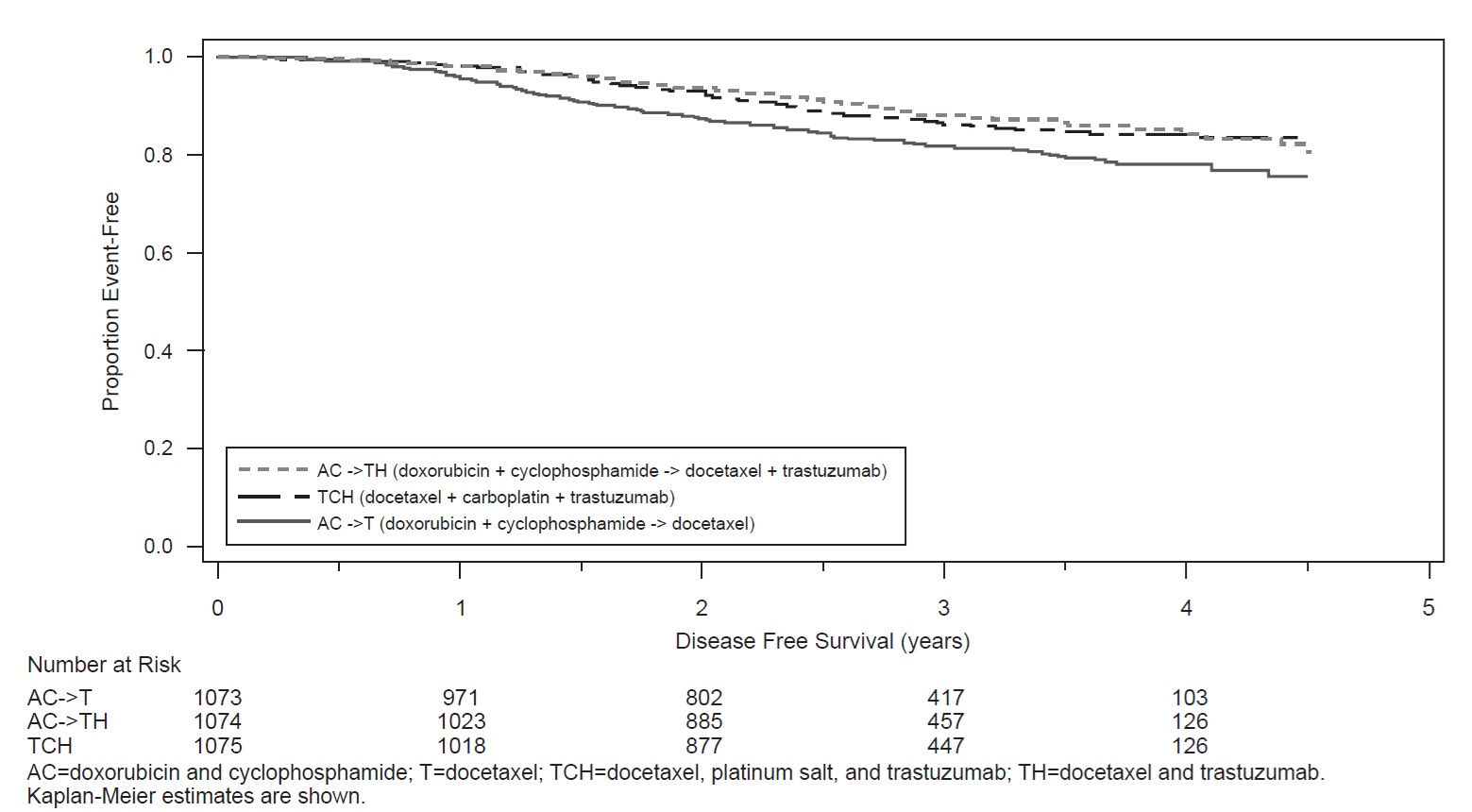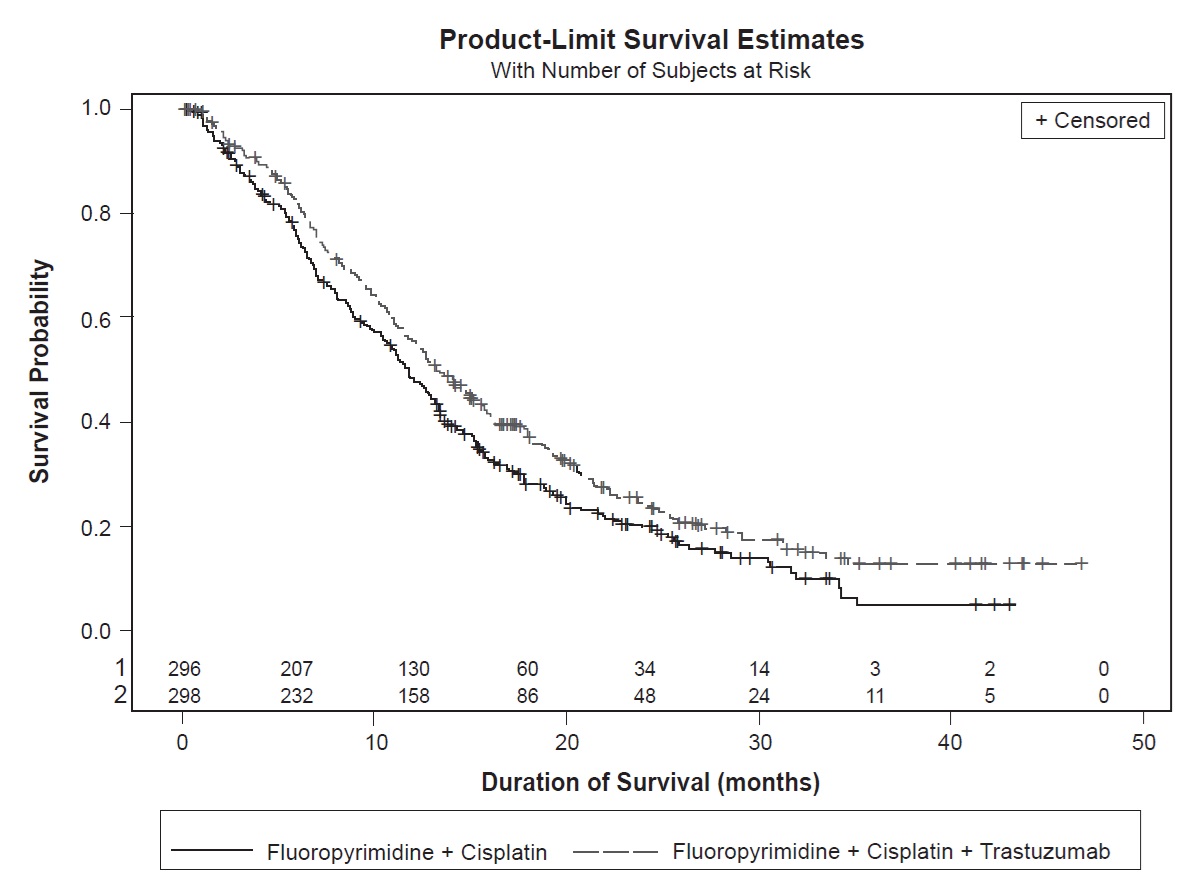 DRUG LABEL: OGIVRI
NDC: 83257-004 | Form: KIT | Route: INTRAVENOUS
Manufacturer: Biocon Biologics Inc.
Category: prescription | Type: HUMAN PRESCRIPTION DRUG LABEL
Date: 20241130

ACTIVE INGREDIENTS: TRASTUZUMAB 420 mg/20 mL
INACTIVE INGREDIENTS: HISTIDINE MONOHYDROCHLORIDE 9.4 mg/20 mL; HISTIDINE 6.0 mg/20 mL; POLYETHYLENE GLYCOL 3350 94.1 mg/20 mL; SORBITOL 322.6 mg/20 mL; BENZYL ALCOHOL 11 mg/20 mL

HIGHLIGHTS OF PRESCRIBING INFORMATION

These highlights do not include all the information needed to use OGIVRI safely and effectively. See full prescribing information for OGIVRI.
OGIVRI® (trastuzumab-dkst) for injection, for intravenous use
Initial U.S. Approval: 2017
OGIVRI® (trastuzumab-dkst) is biosimilar* to HERCEPTIN (trastuzumab).

RECENT MAJOR CHANGES

Dosage and Administration, Evaluation

and Testing Before Initiating Ogivri (2.1) 11/2024

WARNING: CARDIOMYOPATHY, INFUSION REACTIONS, EMBRYO-FETAL TOXICITY, and PULMONARY TOXICITY

See full prescribing information for complete boxed warning

Cardiomyopathy: Trastuzumab products can result in subclinical and clinical cardiac failure manifesting as CHF, and decreased LVEF, with greatest risk when administered concurrently with anthracyclines. Evaluate cardiac function prior to and during treatment. Discontinue Ogivri for cardiomyopathy. (2.5, 5.1)

Infusion Reactions, Pulmonary Toxicity: Discontinue Ogivri for anaphylaxis, angioedema, interstitial pneumonitis, or acute respiratory distress syndrome. (5.2, 5.4)

Embryo-Fetal Toxicity: Exposure to trastuzumab products during pregnancy can result in oligohydramnios, in some cases complicated by pulmonary hypoplasia and neonatal death. Advise patients of these risks and the need for effective contraception. (5.3, 8.1, 8.3)

1 INDICATIONS AND USAGE

Ogivri is a HER2/neu receptor antagonist indicated in adults for:

- The treatment of HER2-overexpressing breast cancer. (1.1, 1.2)
- The treatment of HER2-overexpressing metastatic gastric or gastroesophageal junction adenocarcinoma. (1.3)

Select patients for therapy based on an FDA-approved companion diagnostic for a trastuzumab product (1, 2.2).

2 DOSAGE AND ADMINISTRATION

For intravenous (IV) infusion only. Do not administer as an IV push or bolus. Ogivri has different dosage and administration instructions than subcutaneous trastuzumab products. (2.3)

Do not substitute Ogivri (trastuzumab-dkst) for or with ado-trastuzumab emtansine or fam-trastuzumab deruxtecan. (2.3)

Perform HER2 testing using FDA-approved tests by laboratories with demonstrated proficiency. (1, 2.2)

Adjuvant Treatment of HER2-Overexpressing Breast Cancer (2.2)

Administer at either:

- Initial dose of 4 mg/kg over 90 minutes IV infusion, then 2 mg/kg over 30 minutes IV infusion weekly for 12 weeks (with paclitaxel or docetaxel) or 18 weeks (with docetaxel and carboplatin). One week after the last weekly dose of Ogivri, administer 6 mg/kg as an IV infusion over 30 to 90 minutes every three weeks to complete a total of 52 weeks of therapy, or
- Initial dose of 8 mg/kg over 90 minutes IV infusion, then 6 mg/kg over 30 to 90 minutes IV infusion every three weeks for 52 weeks.

Metastatic HER2-Overexpressing Breast Cancer (2.3)

- Initial dose of 4 mg/kg as a 90 minutes IV infusion followed by subsequent weekly doses of 2 mg/kg as 30 minutes IV infusions.

Metastatic HER2-Overexpressing Gastric Cancer (2.3)

- Initial dose of 8 mg/kg over 90 minutes IV infusion, followed by 6 mg/kg over 30 to 90 minutes IV infusion every 3 weeks.

3 DOSAGE FORMS AND STRENGTHS

- For Injection: 150 mg lyophilized powder in a single-dose vial for reconstitution (3)
- For Injection: 420 mg lyophilized powder in a multiple-dose vial for reconstitution supplied with a separate vial containing 20 mL of Bacteriostatic Water for Injection, USP, to be used as a diluent. (3)
- For Injection: 420 mg lyophilized powder in a multiple-dose vial for reconstitution. No diluent is provided. (3)

4 CONTRAINDICATIONS

- None. (4)

5 WARNINGS AND PRECAUTIONS

- Exacerbation of Chemotherapy-Induced Neutropenia. (5.5, 6.1)

6 ADVERSE REACTIONS

Adjuvant Breast Cancer

- Most common adverse reactions (≥ 5%) are headache, diarrhea, nausea, and chills. (6.1)

Metastatic Breast Cancer

- Most common adverse reactions (≥ 10%) are fever, chills, headache, infection, congestive heart failure, insomnia, cough, and rash. (6.1)

Metastatic Gastric Cancer

- Most common adverse reactions (≥ 10%) are neutropenia, diarrhea, fatigue, anemia, stomatitis, weight loss, upper respiratory tract infections, fever, thrombocytopenia, mucosal inflammation, nasopharyngitis, and dysgeusia. (6.1)

To report SUSPECTED ADVERSE REACTIONS, contact Biocon Biologics at 1-833-986-1468 or FDA at 1-800-FDA-1088 or www.fda.gov/medwatch.

8 USE IN SPECIFIC POPULATIONS

Females and Males of Reproductive Potential: Verify the pregnancy status of females prior to initiation of Ogivri (8.3).

*Biosimilar means that the biological product is approved based on data demonstrating that it is highly similar to an FDA-approved biological product, known as a reference product, and that there are no clinically meaningful differences between the biosimilar product and the reference product. Biosimilarity of Ogivri has been demonstrated for the condition(s) of use (e.g. indication(s), dosing regimen(s)), strength(s), dosage form(s), and route(s) of administration described in its Full Prescribing Information.

FULL PRESCRIBING INFORMATION

WARNING: CARDIOMYOPATHY, INFUSION REACTIONS, EMBRYO-FETAL TOXICITY, and PULMONARY TOXICITY

Cardiomyopathy

Administration of trastuzumab products can result in sub-clinical and clinical cardiac failure. The incidence and severity was highest in patients receiving trastuzumab with anthracycline-containing chemotherapy regimens.

Evaluate left ventricular function in all patients prior to and during treatment with Ogivri. Discontinue Ogivri treatment in patients receiving adjuvant therapy and withhold Ogivri in patients with metastatic disease for clinically significant decrease in left ventricular function [see Dosage and Administration (2.5) and Warnings and Precautions (5.1)].

Infusion Reactions; Pulmonary Toxicity

Administration of trastuzumab products can result in serious and fatal infusion reactions and pulmonary toxicity. Symptoms usually occur during or within 24 hours of administration of trastuzumab products. Interrupt Ogivri infusion for dyspnea or clinically significant hypotension. Monitor patients until symptoms completely resolve. Discontinue Ogivri for anaphylaxis, angioedema, interstitial pneumonitis, or acute respiratory distress syndrome [see Warnings and Precautions (5.2, 5.4)].

Embryo-Fetal Toxicity

Exposure to trastuzumab products during pregnancy can result in oligohydramnios and oligohydramnios sequence manifesting as pulmonary hypoplasia, skeletal abnormalities, and neonatal death. Advise patients of these risks and the need for effective contraception [see Warnings and Precautions (5.3) and Use in Specific Populations (8.1, 8.3)].

1 INDICATIONS AND USAGE

1.1 Adjuvant Breast Cancer

Ogivri is indicated in adults for adjuvant treatment of HER2 overexpressing node positive or node negative (ER/PR negative or with one high risk feature [see Clinical Studies (14.1)]) breast cancer

- as part of a treatment regimen consisting of doxorubicin, cyclophosphamide, and either paclitaxel or docetaxel
- as part of a treatment regimen with docetaxel and carboplatin
- as a single agent following multi-modality anthracycline based therapy.

Select patients for therapy based on an FDA-approved companion diagnostic for a trastuzumab product [see Dosage and Administration (2.2)].

1.2 Metastatic Breast Cancer

Ogivri is indicated in adults:

- In combination with paclitaxel for first-line treatment of HER2-overexpressing metastatic breast cancer
- As a single agent for treatment of HER2-overexpressing breast cancer in patients who have received one or more chemotherapy regimens for metastatic disease.

Select patients for therapy based on an FDA-approved companion diagnostic for a trastuzumab product [see Dosage and Administration (2.2)].

1.3 Metastatic Gastric Cancer

Ogivri is indicated in adults, in combination with cisplatin and capecitabine or 5-fluorouracil, for the treatment of patients with HER2-overexpressing metastatic gastric or gastroesophageal junction adenocarcinoma who have not received prior treatment for metastatic disease.

Select patients for therapy based on an FDA-approved companion diagnostic for a trastuzumab product [see Dosage and Administration (2.2)].

2 DOSAGE AND ADMINISTRATION

2.1 Evaluation and Testing Before Initiating Ogivri

Assess left ventricular ejection fraction (LVEF) prior to initiation of Ogivri and at regular intervals during treatment. [see Boxed Warning, Dosage and Administration (2.5), Warnings and Precautions (5.1)].

Verify the pregnancy status of females of reproductive potential prior to the initiation of Ogivri [see Warnings and Precautions (5.3), Use in Specific Populations (8.1, 8.3)].

2.2 Patient Selection

Select patients based on HER2 protein overexpression or HER2 gene amplification in tumor specimens [see Indications and Usage (1) and Clinical Studies (14)]. Assessment of HER2 protein overexpression and HER2 gene amplification should be performed using FDA-approved tests specific for breast or gastric cancers by laboratories with demonstrated proficiency. Information on the FDA-approved tests for the detection of HER2 protein overexpression and HER2 gene amplification is available at: http://www.fda.gov/CompanionDiagnostics.

Assessment of HER2 protein overexpression and HER2 gene amplification in metastatic gastric cancer should be performed using FDA-approved tests specifically for gastric cancers due to differences in gastric vs. breast histopathology, including incomplete membrane staining and more frequent heterogeneous expression of HER2 seen in gastric cancers.

Improper assay performance, including use of suboptimally fixed tissue, failure to utilize specified reagents, deviation from specific assay instructions, and failure to include appropriate controls for assay validation, can lead to unreliable results.

2.3 Recommended Dosage

- Ogivri is for intravenous infusion only. Do not administer as an intravenous push or bolus.
- Ogivri has different dosage and administration instructions than subcutaneous trastuzumab products.
- Do not mix Ogivri with other drugs.
- Do not substitute Ogivri (trastuzumab-dkst) for or with ado-trastuzumab emtansine or fam-trastuzumab deruxtecan.

Adjuvant Treatment of Breast Cancer:

Administer according to one of the following doses and schedules for a total of 52 weeks of Ogivri therapy:

During and following paclitaxel, docetaxel, or docetaxel and carboplatin:

Initial dose of 4 mg/kg as an intravenous infusion over 90 minutes then at 2 mg/kg as an intravenous infusion over 30 minutes weekly during chemotherapy for the first 12 weeks (paclitaxel or docetaxel) or 18 weeks (docetaxel and carboplatin).

- One week following the last weekly dose of Ogivri, administer Ogivri at 6 mg/kg as an intravenous infusion over 30 to 90 minutes every three weeks.

As a single agent within three weeks following completion of multi-modality, anthracycline-based chemotherapy regimens:

- Initial dose at 8 mg/kg as an intravenous infusion over 90 minutes
- Subsequent doses at 6 mg/kg as an intravenous infusion over 30 to 90 minutes every three weeks.
- Extending adjuvant treatment beyond one year is not recommended [see Adverse Reactions (6.1)].

Metastatic Breast Cancer:

- Administer Ogivri, alone or in combination with paclitaxel, at an initial dose of 4 mg/kg as a 90-minute intravenous infusion followed by subsequent once weekly doses of 2 mg/kg as 30-minute intravenous infusions until disease progression.

Metastatic Gastric Cancer:

- Administer Ogivri at an initial dose of 8 mg/kg as a 90 minute intravenous infusion followed by subsequent doses of 6 mg/kg as an intravenous infusion over 30 to 90 minutes every three weeks until disease progression.

2.4 Important Dosing Considerations

Missed Dose

If the patient has missed a dose of Ogivri by one week or less, then the usual maintenance dose (weekly schedule: 2 mg/kg; once every three weeks schedule: 6 mg/kg) should be administered as soon as possible. Do not wait until the next planned cycle. Subsequent Ogivri maintenance doses should be administered 7 days or 21 days later according to the weekly or once every three week schedules, respectively.

If the patient has missed a dose of Ogivri by more than one week, a re-loading dose of Ogivri should be administered over approximately 90 minutes (weekly schedule: 4 mg/kg; once every three week schedule: 8 mg/kg) as soon as possible. Subsequent Ogivri maintenance doses (weekly schedule: 2 mg/kg; three-weekly schedule 6 mg/kg) should be administered 7 days or 21 days later according to the weekly or once every three week schedules, respectively.

2.5 Dosage Modifications for Adverse Reactions

Infusion Reactions

[see Boxed Warning, Warnings and Precautions (5.2)]

- Decrease the rate of infusion for mild or moderate infusion reactions
- Interrupt the infusion in patients with dyspnea or clinically significant hypotension
- Discontinue Ogivri for severe or life-threatening infusion reactions.

Cardiomyopathy

[see Boxed Warning, Warnings and Precautions (5.1)]

Assess left ventricular ejection fraction (LVEF) prior to initiation of Ogivri and at regular intervals during treatment. Withhold Ogivri dosing for at least 4 weeks for either of the following:

- ≥16% absolute decrease in LVEF from pre-treatment values
- LVEF below institutional limits of normal and ≥ 10% absolute decrease in LVEF from pretreatment values.

Ogivri may be resumed if, within 4 to 8 weeks, the LVEF returns to normal limits and the absolute decrease from baseline is ≤15%.

Permanently discontinue Ogivri for a persistent (>8 weeks) LVEF decline or for suspension of Ogivri dosing on more than 3 occasions for cardiomyopathy.

2.6 Preparation Instructions

To prevent medication errors, it is important to check the vial labels to ensure that the drug being prepared and administered is Ogivri (trastuzumab-dkst) and not ado-trastuzumab emtansine or fam- trastuzumab deruxtecan.

420 mg Multiple-dose vial supplied with a separate vial containing 20 mL of Bacteriostatic Water for Injection, USP, to be used as diluent.

420 mg Multiple-dose vial drug only carton. No diluent is provided.

Reconstitution: Reconstitute each 420 mg vial of Ogivri with 20 mL of Bacteriostatic Water for Injection, USP (BWFI), containing 0.9% to 1.1% benzyl alcohol (not supplied for the 420 mg multiple-dose vial drug only carton) as a preservative to yield a multiple-dose solution containing 21 mg/mL trastuzumab-dkst that delivers 20 mL (420 mg trastuzumab-dkst). In patients with known hypersensitivity to benzyl alcohol, reconstitute with 20 mL of Sterile Water for Injection, USP (SWFI) without preservative to yield a one-time use solution.

Use appropriate aseptic technique when performing the following reconstitution steps:

- Using a sterile syringe, slowly inject the 20 mL of diluent into the vial containing the lyophilized powder of Ogivri, which has a cake-like appearance. The stream of diluent should be directed into the lyophilized cake. The reconstituted vial yields a solution for multiple-dose use, containing 21 mg/mL trastuzumab-dkst.
- Swirl the vial gently to aid reconstitution. DO NOT SHAKE.
- Slight foaming of the product may be present upon reconstitution. Allow the vial to stand undisturbed for approximately 5 minutes.
- Parenteral drug products should be inspected visually for particulate matter and discoloration prior to administration, whenever solution and container permit. Inspect visually for particulates and discoloration. The solution should be free of visible particulates, clear to slightly opalescent and colorless to pale yellow.
- Store reconstituted Ogivri in the refrigerator at 2° to 8°C (36° to 46°F); discard unused Ogivri after 28 days. If Ogivri is reconstituted with SWFI without preservative, use immediately and discard any unused portion. Do not freeze.

Dilution:

- Determine the dose (mg) of Ogivri [see Dosage and Administration (2.3)]. Calculate the volume of the 21 mg/mL reconstituted Ogivri solution needed.
- Withdraw this amount from the vial using a sterile needle and syringe and add it to an infusion bag containing 250 mL of 0.9% Sodium Chloride Injection, USP. DO NOT USE DEXTROSE (5%) SOLUTION.
- Gently invert the bag to mix the solution.
- The solution of Ogivri for infusion diluted in polyvinylchloride or polyethylene bags containing 0.9% Sodium Chloride Injection, USP, should be stored at 2° to 8°C (36° to 46°F) for no more than 24 hours prior to use. This storage time is additional to the time allowed for the reconstituted vials. Do not freeze.

150 mg Single-dose vial

Reconstitution: Reconstitute each 150 mg vial of Ogivri with 7.4 mL of Sterile Water for Injection (SWFI) (not supplied) to yield a single-dose solution containing 21 mg/mL trastuzumab-dkst that delivers 7.15 mL (150 mg trastuzumab-dkst).

Use appropriate aseptic technique when performing the following reconstitution steps:

- Using a sterile syringe, slowly inject 7.4 mL of SWFI (not supplied) into the vial containing the lyophilized powder of Ogivri, which has a cake-like appearance. The stream of diluent should be directed into the cake. The reconstituted vial yields a solution containing 21 mg/mL trastuzumab-dkst.
- Swirl the vial gently to aid reconstitution. DO NOT SHAKE.
- Slight foaming of the product may be present upon reconstitution. Allow the vial to stand undisturbed for approximately 5 minutes.
- Parenteral drug products should be inspected visually for particulate matter and discoloration prior to administration, whenever solution and container permit. Inspect visually for particulates and discoloration. The solution should be free of visible particulates, clear to slightly opalescent and colorless to pale yellow.
- Use the Ogivri solution immediately following reconstitution with SWFI, as it contains no preservative and is intended for one-time use only. If not used immediately, store the reconstituted Ogivri solution for up to 24 hours at 2° to 8°C (36° to 46°F); discard any unused Ogivri after 24 hours. Do not freeze.

Dilution:

- Determine the dose (mg) of Ogivri [see Dosage and Administration (2.3)].
- Calculate the volume of the 21 mg/mL reconstituted Ogivri solution needed
- Withdraw this amount from the vial using a sterile needle and syringe and add it to an infusion bag containing 250 mL of 0.9% Sodium Chloride Injection, USP. DO NOT USE DEXTROSE (5%) SOLUTION.
- Gently invert the bag to mix the solution.
- The solution of Ogivri for infusion diluted in polyvinylchloride or polyethylene bags containing 0.9% Sodium Chloride Injection, USP, should be stored at 2° to 8°C (36° to 46°F) for no more than 24 hours prior to use. Discard after 24 hours. This storage time is additional to the time allowed for the reconstituted vials. Do not freeze.

3 DOSAGE FORMS AND STRENGTHS

- For injection: 150 mg of Ogivri as an off-white to pale yellow lyophilized powder in a single-dose vial.
- For injection: 420 mg of Ogivri as an off-white to pale yellow lyophilized powder in a multiple-dose vial supplied with a separate vial containing 20 mL of Bacteriostatic Water for Injection (BWFI), to be used as a diluent.
- For injection: 420 mg of Ogivri as an off-white to pale yellow lyophilized powder in a multiple-dose vial. No diluent is provided.

4 CONTRAINDICATIONS

None.

5 WARNINGS AND PRECAUTIONS

5.1 Cardiomyopathy

Trastuzumab products can cause left ventricular cardiac dysfunction, arrhythmias, hypertension, disabling cardiac failure, cardiomyopathy, and cardiac death [see Boxed Warning: Cardiomyopathy]. Trastuzumab products can also cause asymptomatic decline in left ventricular ejection fraction (LVEF).

There is a 4 to 6 fold increase in the incidence of symptomatic myocardial dysfunction among patients receiving trastuzumab products as a single agent or in combination therapy compared with those not receiving trastuzumab products. The highest absolute incidence occurs when a trastuzumab product is administered with an anthracycline.

Withhold Ogivri for ≥ 16% absolute decrease in LVEF from pre-treatment values or an LVEF value below institutional limits of normal and ≥ 10% absolute decrease in LVEF from pretreatment values [see Dosage and Administration (2.5)]. The safety of continuation or resumption of trastuzumab products in patients with trastuzumab product-induced left ventricular cardiac dysfunction has not been studied.

Patients who receive anthracycline after stopping trastuzumab products may also be at increased risk of cardiac dysfunction [see Drug Interactions (7) and Clinical Pharmacology (12.3)].

Cardiac Monitoring

Conduct thorough cardiac assessment, including history, physical examination, and determination of LVEF by echocardiogram or MUGA scan. The following schedule is recommended:

- Baseline LVEF measurement immediately prior to initiation of Ogivri
- LVEF measurements every 3 months during and upon completion of Ogivri
- Repeat LVEF measurement at 4 week intervals if Ogivri is withheld for significant left ventricular cardiac dysfunction [see Dosage and Administration (2.5)]
- LVEF measurements every 6 months for at least 2 years following completion of Ogivri as a component of adjuvant therapy.

In NSABP B31, 15% (158/1031) of patients discontinued trastuzumab due to clinical evidence of myocardial dysfunction or significant decline in LVEF after a median follow-up duration of 8.7 years in the AC-TH (anthracycline, cyclophosphamide, paclitaxel, and trastuzumab) arm. In HERA (one-year trastuzumab treatment), the number of patients who discontinued trastuzumab due to cardiac toxicity at 12.6 months median duration of follow-up was 2.6% (44/1678). In BCIRG006, a total of 2.9% (31/1056) of patients in the TCH (docetaxel, carboplatin, trastuzumab) arm (1.5% during the chemotherapy phase and 1.4% during the monotherapy phase) and 5.7% (61/1068) of patients in the AC-TH arm (1.5% during the chemotherapy phase and 4.2% during the monotherapy phase) discontinued trastuzumab due to cardiac toxicity.

Among 64 patients receiving adjuvant chemotherapy (NSABP B31 and NCCTG N9831) who developed congestive heart failure, one patient died of cardiomyopathy, one patient died suddenly without documented etiology and 33 patients were receiving cardiac medication at last follow-up. Approximately 24% of the surviving patients had recovery to a normal LVEF (defined as ≥ 50%) and no symptoms on continuing medical management at the time of last follow-up. Incidence of congestive heart failure (CHF) is presented in Table 1. The safety of continuation or resumption of trastuzumab products in patients with trastuzumab product-induced left ventricular cardiac dysfunction has not been studied.

Table 1: Incidence of Congestive Heart Failure in Adjuvant Breast Cancer Studies

 |  | Incidence of Congestive Heart Failure; % (n)
Study | Regimen | Trastuzumab | Control
NSABP; B31 & NCCTG N9831a | ACb → Paclitaxel + Trastuzumab | 3.2% (64/2000)c | 1.3% (21/1655)
HERAd | Chemotherapy →Trastuzumab | 2% (30/1678) | 0.3% (5/1708)
BCIRG0; 06 | ACb → Docetaxel + Trastuzumab | 2% (20/1068) | 0.3% (3/1050)
BCIRG0; 06 | Docetaxel + Carboplatin + Trastuzumab | 0.4% (4/1056) | 0.3% (3/1050)

a Median follow-up duration for NSABP B31 & NCCTG N9831 combined was 8.3 years in the AC → paclitaxel + trastuzumab arm.

b Anthracycline (doxorubicin) and cyclophosphamide.

c Includes 1 patient with fatal cardiomyopathy and 1 patient with sudden death without documented etiology.

d Includes NYHA II-IV and cardiac death at 12.6 months median duration of follow-up in the one-year trastuzumab arm.

In HERA (one-year trastuzumab treatment), at a median follow-up duration of 8 years, the incidence of severe CHF (NYHA III & IV) was 0.8%, and the rate of mild symptomatic and asymptomatic left ventricular dysfunction was 4.6%.

Table 2:Incidence of Cardiac Dysfunctiona in Metastatic Breast Cancer Studies

 |  | Incidence
 |  | NYHA I−IV |  | NYHA III−IV
Study | Event | Trastuzumab | Control | Trastuzumab | Control
H0648g (AC)b | Cardiac Dysfunction | 28% | 7% | 19% | 3%
H0648g; (paclitaxel) | Cardiac Dysfunction | 11% | 1% | 4% | 1%
H0649g | Cardiac Dysfunctionc | 7% | N/A | 5% | N/A

a Congestive heart failure or significant asymptomatic decrease in LVEF.

b Anthracycline (doxorubicin or epirubicin) and cyclophosphamide.

c Includes 1 patient with fatal cardiomyopathy.

In BCIRG006, the incidence of NCI-CTC Grade 3/4 cardiac ischemia/infarction was higher in the trastuzumab containing regimens (AC-TH: 0.3% (3/1068) and TCH: 0.2% (2/1056)) as compared to none in AC-T.

5.2 Infusion Reactions

Infusion reactions consist of a symptom complex characterized by fever and chills, and on occasion included nausea, vomiting, pain (in some cases at tumor sites), headache, dizziness, dyspnea, hypotension, rash, and asthenia [see Adverse Reactions (6.1)].

In post-marketing reports, serious and fatal infusion reactions have been reported. Severe reactions, which include bronchospasm, anaphylaxis, angioedema, hypoxia, and severe hypotension, were usually reported during or immediately following the initial infusion. However, the onset and clinical course were variable, including progressive worsening, initial improvement followed by clinical deterioration, or delayed post-infusion events with rapid clinical deterioration. For fatal events, death occurred within hours to days following a serious infusion reaction.

Interrupt Ogivri infusion in all patients experiencing dyspnea, clinically significant hypotension, and intervention of medical therapy administered (which may include epinephrine, corticosteroids, diphenhydramine, bronchodilators, and oxygen). Patients should be evaluated and carefully monitored until complete resolution of signs and symptoms. Permanent discontinuation should be strongly considered in all patients with severe infusion reactions.

There are no data regarding the most appropriate method of identification of patients who may safely be retreated with trastuzumab products after experiencing a severe infusion reaction. Prior to resumption of trastuzumab infusion, the majority of patients who experienced a severe infusion reaction were pre-medicated with antihistamines and/or corticosteroids. While some patients tolerated trastuzumab infusions, others had recurrent severe infusion reactions despite pre-medications.

5.3 Embryo-Fetal Toxicity

Trastuzumab products can cause fetal harm when administered to a pregnant woman. In post-marketing reports, use of trastuzumab during pregnancy resulted in cases of oligohydramnios and oligohydramnios sequence manifesting as pulmonary hypoplasia, skeletal abnormalities, and neonatal death.

Verify the pregnancy status of females of reproductive potential prior to the initiation of Ogivri. Advise pregnant women and females of reproductive potential that exposure to Ogivri during pregnancy or within 7 months prior to conception can result in fetal harm. Advise females of reproductive potential to use effective contraception during treatment and for 7 months following the last dose of Ogivri [see Use in Specific Populations (8.1, 8.3) and Clinical Pharmacology (12.3)].

5.4 Pulmonary Toxicity

Trastuzumab product use can result in serious and fatal pulmonary toxicity. Pulmonary toxicity includes dyspnea, interstitial pneumonitis, pulmonary infiltrates, pleural effusions, non-cardiogenic pulmonary edema, pulmonary insufficiency and hypoxia, acute respiratory distress syndrome, and pulmonary fibrosis. Such events can occur as sequelae of infusion reactions [see Warnings and Precautions (5.2)]. Patients with symptomatic intrinsic lung disease or with extensive tumor involvement of the lungs, resulting in dyspnea at rest, appear to have more severe toxicity.

5.5 Exacerbation of Chemotherapy-Induced Neutropenia

In randomized, controlled clinical trials, the per-patient incidences of NCI-CTC Grade 3 to 4 neutropenia and of febrile neutropenia were higher in patients receiving trastuzumab in combination with myelosuppressive chemotherapy as compared to those who received chemotherapy alone. The incidence of septic death was similar among patients who received trastuzumab and those who did not [see Adverse Reactions (6.1)].

6 ADVERSE REACTIONS

The following adverse reactions are discussed in greater detail in other sections of the label:

- Cardiomyopathy [see Warnings and Precautions (5.1)]
- Infusion Reactions [see Warnings and Precautions (5.2)]
- Embryo-Fetal Toxicity [see Warnings and Precautions (5.3)]
- Pulmonary Toxicity [see Warnings and Precautions (5.4)]
- Exacerbation of Chemotherapy-induced Neutropenia [see Warnings and Precautions (5.5)]

6.1 Clinical Trials Experience

Because clinical trials are conducted under widely varying conditions, adverse reaction rates observed in the clinical trials of a drug cannot be directly compared to rates in the clinical trials of another drug and may not reflect the rates observed in practice.

The most common adverse reactions in patients receiving trastuzumab products in the adjuvant and metastatic breast cancer setting are fever, nausea, vomiting, infusion reactions, diarrhea, infections, increased cough, headache, fatigue, dyspnea, rash, neutropenia, anemia, and myalgia. Adverse reactions requiring interruption or discontinuation of trastuzumab product treatment include CHF, significant decline in left ventricular cardiac function, severe infusion reactions, and pulmonary toxicity [see Dosage and Administration (2.5)].

In the metastatic gastric cancer setting, the most common adverse reactions (≥ 10%) that were increased (≥ 5% difference) in the trastuzumab arm as compared to the chemotherapy alone arm were neutropenia, diarrhea, fatigue, anemia, stomatitis, weight loss, upper respiratory tract infections, fever, thrombocytopenia, mucosal inflammation, nasopharyngitis, and dysgeusia.

The most common adverse reactions which resulted in discontinuation of treatment on the trastuzumab-containing arm in the absence of disease progression were infection, diarrhea, and febrile neutropenia.

Adjuvant Breast Cancer

The information below reflects exposure to one-year trastuzumab therapy across three randomized, open-label studies, NSABP B31, NCCTG N9831, and HERA, with (n = 3678) or without (n = 3363) trastuzumab in the adjuvant treatment of breast cancer.

HERA

Table 3 reflects exposure to trastuzumab in 1678 patients in HERA; the median treatment duration was 51 weeks and median number of infusions was 18 [see Clinical Studies (14.1)].

Table 3: Adverse Reactions (>1%) in HERA (All Grades)a

Adverse Reactions | Trastuzumab; (n = 1678); % | Observation; (n = 1708); %
Nervous System
Headache | 10 | 3
Paresthesia | 2 | 0.6
Musculoskeletal
Arthralgia | 8 | 6
Back pain | 5 | 3
Myalgia | 4 | 1
Bone pain | 3 | 2
Muscle spasm | 3 | 0.2
Infections
Nasopharyngitis | 8 | 3
Urinary tract infection | 3 | 0.8
Gastrointestinal
Diarrhea | 7 | 1
Nausea | 6 | 1
Vomiting | 3.5 | 0.6
Constipation | 2 | 1
Dyspepsia | 2 | 0.5
Upper abdominal pain | 2 | 1
General
Pyrexia | 6 | 0.4
Peripheral edema | 5 | 2
Chills | 5 | 0
Asthenia | 4.5 | 2
Influenza-like illness | 2 | 0.2
Respiratory Thoracic Mediastinal
Cough | 5 | 2
Influenza | 4 | 0.5
Dyspnea | 3 | 2
URI | 3 | 1
Rhinitis | 2 | 0.4
Pharyngolaryngeal pain | 2 | 0.5
Sinusitis | 2 | 0.3
Epistaxis | 2 | 0.06
Cardiac
Hypertension | 4 | 2
Dizziness | 4 | 2
Ejection fraction decreased | 3.5 | 0.6
Palpitations | 3 | 0.7
Cardiac arrhythmiasb | 3 | 1
Cardiac failure (congestive) | 2 | 0.3
Skin & Subcutaneous Tissue
Rash | 4 | 0.6
Nail disorders | 2 | 0
Pruritus | 2 | 0.6

aThe incidence of Grade 3 or higher adverse reactions was < 1% in both arms for each listed term.

b Higher level grouping term.

Clinically relevant adverse reactions in < 1% of patients who received trastuzumab in HERA included hypersensitivity (0.6%), cardiac failure (0.5%), cardiac disorder (0.3%), interstitial pneumonitis (0.2%), pulmonary hypertension (0.2%), ventricular disorder (0.2%), autoimmune thyroiditis (0.3%), and sudden death (0.06%).

Adjuvant Treatment of Breast Cancer with Trastuzumab Beyond One Year

Extending adjuvant treatment beyond one year is not recommended [see Dosage and Administration (2.3)]. In HERA, a comparison of trastuzumab administered once every 3 weeks for two years versus one year was performed. The rate of asymptomatic cardiac dysfunction was increased in the 2-year trastuzumab compared to the 1-year trastuzumab treatment arm (8.1% versus 4.6%, respectively). More patients experienced at least one adverse reaction of Grade 3 or higher in the 2-year trastuzumab treatment arm (20.4%) compared with the one-year trastuzumab treatment arm (16.3%).

NSABP B31 and NCCTG N9831

The safety data from NSABP B31 and NCCTG N9831 were obtained from 3655 patients, of whom 2000 received trastuzumab; the median treatment duration was 51 weeks [see Clinical Studies (14.1)].

In NSABP B31, only Grade 3 to 5 adverse events, treatment-related Grade 2 events, and Grade 2 to 5 dyspnea were collected during and for up to 3 months following protocol-specified treatment. The following non-cardiac adverse reactions of Grade 2 to 5 occurred at an incidence of at least 2% greater among patients receiving trastuzumab plus chemotherapy as compared to chemotherapy alone: fatigue (29.5% vs. 22.4%), infection (24.0% vs. 12.8%), hot flashes (17.1% vs. 15%), anemia (12.3% vs. 6.7%), dyspnea (11.8% vs. 4.6%), rash/desquamation (10.9% vs. 7.6%), leukopenia (10.5% vs. 8.4%), neutropenia (6.4% vs. 4.3%), headache (6.2% vs. 3.8%), pain (5.5% vs. 3%), edema (4.7% vs. 2.7%) and insomnia (4.3% vs. 1.5%). The majority of these events were Grade 2 in severity.

In NCCTG N9831, data collection was limited to the following investigator-attributed treatment-related adverse reactions: NCI-CTC Grade 4 and 5 hematologic toxicities, Grade 3 to 5 non-hematologic toxicities, selected Grade 2 to 5 toxicities associated with taxanes (myalgia, arthralgias, nail changes, motor neuropathy, and sensory neuropathy) and Grade 1 to 5 cardiac toxicities occurring during chemotherapy and/or trastuzumab treatment. The following non-cardiac adverse reactions of Grade 2 to 5 occurred at an incidence of at least 2% greater among patients receiving trastuzumab plus chemotherapy as compared to chemotherapy alone: arthralgia (12.2% vs. 9.1%), nail changes (11.5% vs.6.8%), dyspnea (2.4% vs. 0.2%), and diarrhea (2.2% vs. 0%). The majority of these events were Grade 2 in severity.

BCIRG006

Safety data from BCIRG006reflect exposure to trastuzumab as part of an adjuvant treatment regiimen from 2124 patients receiving at least one dose of study treatment [AC-TH: n = 1068; TCH: n = 1056]. The overall median treatment duration was 54 weeks in both the AC-TH and TCH arms. The median number of infusions was 26 in the AC-TH arm and 30 in the TCH arm, including weekly infusions during the chemotherapy phase and once every three week dosing in the monotherapy period [see Clinical Studies (14.1)]. In BCIRG006, the toxicity profile was similar to that reported in NSABP B31, NCCTG N9831, and HERA with the exception of a lower incidence of CHF in the TCH arm.

Metastatic Breast Cancer Studies

The safety of trastuzumab was evaluated in one randomized, open-label study (H0648g) of chemotherapy with (n = 235) or without (n = 234) intravenous trastuzumab in patients with metastatic breast cancer and in one single-arm study (H0649g); in patients with metastatic breast cancer (n=222) [see Clinical Studies (14.1)]. Patients received 4 mg/kg initial dose of trastuzumab followed by 2 mg/kg weekly. In H0648g, 58% of patients received trastuzumab for ≥ 6 months and 9% received trastuzumab ≥ 12 months, respectively. In H0649g, 31% of patients received trastuzumab for ≥ 6 months and 16% received trastuzumab for ≥ 12 months, respectively.

Table 4 shows the adverse reactions (≥ 5%) in patients from H0648g and H0649g.

Table 4: Adverse Reactions³ (5%) in the Trastuzumab Arms in H0648g and H0649g

 | Trastuzumaba n = 352; % | Trastuzumab +; Paclitaxel; n = 91; % | Paclitaxel n = 95; % | Trastuzumab +; ACb; n = 143; % | ACb; n = 135 %
General
Pain | 47 | 61 | 62 | 57 | 42
Asthenia | 42 | 62 | 57 | 54 | 55
Fever | 36 | 49 | 23 | 56 | 34
Chills | 32 | 41 | 4 | 35 | 11
Headache | 26 | 36 | 28 | 44 | 31
Abdominal pain | 22 | 34 | 22 | 23 | 18
Back pain | 22 | 34 | 30 | 27 | 15
Infection | 20 | 47 | 27 | 47 | 31
Flu syndrome | 10 | 12 | 5 | 12 | 6
Accidental injury | 6 | 13 | 3 | 9 | 4
Allergic reaction | 3 | 8 | 2 | 4 | 2
Gastrointestinal
Nausea | 33 | 51 | 9 | 76 | 77
Diarrhea | 25 | 45 | 29 | 45 | 26
Vomiting | 23 | 37 | 28 | 53 | 49
Anorexia | 14 | 24 | 16 | 31 | 26
Nausea and vomiting | 8 | 14 | 11 | 18 | 9
Respiratory
Cough increased | 26 | 41 | 22 | 43 | 29
Dyspnea | 22 | 27 | 26 | 42 | 25
Rhinitis | 14 | 22 | 5 | 22 | 16
Pharyngitis | 12 | 22 | 14 | 30 | 18
Sinusitis | 9 | 21 | 7 | 13 | 6
Skin
Rash | 18 | 38 | 18 | 27 | 17
Herpes simplex | 2 | 12 | 3 | 7 | 9
Acne | 2 | 11 | 3 | 3 | < 1
Nervous
Insomnia | 14 | 25 | 13 | 29 | 15
Dizziness | 13 | 22 | 24 | 24 | 18
Paresthesia | 9 | 48 | 39 | 17 | 11
Depression | 6 | 12 | 13 | 20 | 12
Peripheral neuritis | 2 | 23 | 16 | 2 | 2
Neuropathy | 1 | 13 | 5 | 4 | 4
Metabolic
Peripheral edema | 10 | 22 | 20 | 20 | 17
Edema | 8 | 10 | 8 | 11 | 5
Cardiovascular
Congestive heart failure | 7 | 11 | 1 | 28 | 7
Tachycardia | 5 | 12 | 4 | 10 | 5

Table 4: Adverse Reactions (> 5%) in the Trastuzumab Arms in H0648g and H0649g (continued)

 | Trastuzumaba; n = 352; % | Trastuzumab +; Paclitaxel; n = 91; % | Paclitaxel; n = 95; % | Trastuzumab +; ACb; n = 143; % | ACb; n =135; %
Musculoskeletal
Bone pain | 7 | 24 | 18 | 7 | 7
Arthralgia | 6 | 37 | 21 | 8 | 9
Urogenital
Urinary tract infection | 5 | 18 | 14 | 13 | 7
Blood and Lymphatic
Anemia | 4 | 14 | 9 | 36 | 26
Leukopenia | 3 | 24 | 17 | 52 | 34

a Data for trastuzumab single agent were from 4 studies, including 213 patients from H0649g.

b Anthracycline (doxorubicin or epirubicin) and cyclophosphamide.

Metastatic Gastric Cancer

The safety of trastuzumab was evaluated in patients with previously untreated for metastatic gastric or gastroesophageal junction adenocarcinoma in an open label, multi-center trial (ToGA) [see Clinical Studies (14.3)]. Patients were randomized (1:1) to receive trastuzumab in combination with cisplatin and a fluoropyrimidine (FC+H) (n=294) or chemotherapy alone (FC) (n=290) Patients in the trastuzumab plus chemotherapy arm received trastuzumab 8 mg/kg administered on Day 1 (prior to chemotherapy) followed by 6 mg/kg every 21 days until disease progression. Cisplatin was administered at 80 mg/m^2 on Day 1 and the fluoropyrimidine was administered as either capecitabine 1000 mg/m^2 orally twice a day on Days 1 to 14 or 5-fluorouracil 800 mg/m^2/day as a continuous intravenous infusion Days 1 through 5. Chemotherapy was administered for six 21-day cycles. Median duration of trastuzumab treatment was 21 weeks and the median number of trastuzumab infusions administered was eight.

Table 5: Adverse Reactions (All Grades > 5% or Grade 3-4 > 1% between Arms) in ToGA

Adverse Reactions | Trastuzumab + FC; (N = 294) % |  | FC; (N = 290); %
Adverse Reactions | All Grades | Grades 3 to 4 | All Grades | Grades 3 to 4
Investigations
Neutropenia | 78 | 34 | 73 | 29
Hypokalemia | 28 | 10 | 24 | 6
Anemia | 28 | 12 | 21 | 10
Thrombocytopenia | 16 | 5 | 11 | 3
Blood and Lymphatic System Disorders
Febrile Neutropenia | - | 5 | - | 3
Gastrointestinal Disorders
Diarrhea | 37 | 9 | 28 | 4
Stomatitis | 24 | 1 | 15 | 2
Dysphagia | 6 | 2 | 3 | < 1
General
Fatigue | 35 | 4 | 28 | 2
Fever | 18 | 1 | 12 | 0
Mucosal Inflammation | 13 | 2 | 6 | 1
Chills | 8 | < 1 | 0 | 0
Metabolism and Nutrition Disorders
Weight Decrease | 23 | 2 | 14 | 2
Infections and Infestations
Upper Respiratory Tract Infections | 19 | 0 | 10 | 0
Nasopharyngitis | 13 | 0 | 6 | 0
Renal and Urinary Disorders
Renal Failure and Impairment | 18 | 3 | 15 | 2
Nervous System Disorders
Dysgeusia | 10 | 0 | 5 | 0

The following subsections provide additional detail regarding adverse reactions observed in clinical trials of adjuvant breast cancer, metastatic breast cancer, metastatic gastric cancer, or post-marketing experience.

Cardiomyopathy

Serial measurement of cardiac function (LVEF) was obtained in clinical trials in the adjuvant treatment of breast cancer. In HERA, the median duration of follow-up was 12.6 months (12.4 months in the observation arm; 12.6 months in the 1-year trastuzumab arm); and in NSABP B31 and NCCTG N9831, 7.9 years in the AC-T arm, 8.3 years in the AC-TH arm. Following initiation of trastuzumab therapy, the incidence of new-onset dose-limiting myocardial dysfunction was higher among patients receiving trastuzumab and paclitaxel as compared to those receiving paclitaxel alone in NSABP B31 and NCCTG N9831, and in patients receiving one-year trastuzumab monotherapy compared to observation in HERA (see Table 6, Figures 1 and 2). The incidence of new-onset cardiac dysfunction, as measured by LVEF, remained similar when compared to the analysis performed at a median follow-up of 2.0 years in the AC-TH arm. This analysis showed evidence of reversibility of left ventricular dysfunction, with 64.5% of patients who experienced symptomatic CHF in the AC-TH group being asymptomatic at latest follow-up, and 90.3% having full or partial LVEF recovery.

Table 6: Myocardial Dysfunction (by LVEF) in NSABP B31, NCCTG N9831, HERA and BCIRG006a

Study and Arm | LVEF <50%; and Decrease from Baseline |  |  | LVEF Decrease
 | LVEF; < 50% | ≥ 10%; decrease | ≥ 16%; decrease | < 20% and ≥ 10% | ≥ 20%
NSABP B31 & NCCTGb,c
AC → TH; (n = 1856) | 23.1%; (428) | 18.5%; (344) | 11.2%; (208) | 37.9%; (703) | 8.9%; (166)
AC → T; (n = 1170) | 11.7%; (137) | 7.0%; (82) | 3.0%; (35) | 22.1%; (259) | 3.4%; (40)
HERAd
Trastuzumab; (n = 1678) | 8.6%; (144) | 7.0%; (118) | 3.8%; (64) | 22.4%; (376) | 3.5%; (59)
Observation; (n = 1708) | 2.7%; (46) | 2.0%; (35) | 1.2%; (20) | 11.9%; (204) | 1.2%; (21)
BCIRG006e
TCH; (n = 1056) | 8.5%; (90) | 5.9%; (62) | 3.3%; (35) | 34.5%; (364) | 6.3%; (67)
AC → TH; (n = 1068) | 17%; (182) | 13.3%; (142) | 9.8%; (105) | 44.3%; (473) | 13.2%; (141)
AC → T; (n = 1050) | 9.5%; (100) | 6.6%; (69) | 3.3%; (35) | 34%; (357) | 5.5%; (58)

a For NSABP B31, NCCTG N9831, and HERA, events are counted from the beginning of trastuzumab treatment. For BCIRG006, events are counted from the date of randomization.

b NSABP B31 and NCCTG N9831 regimens: doxorubicin and cyclophosphamide followed by paclitaxel (AC → T) or paclitaxel plus trastuzumab (AC → TH).

c Median duration of follow-up for NSABP B31 and NCCTG N9831 combined was 8.3 years in the AC → TH arm.

d Median follow-up duration of 12.6 months in the one-year trastuzumab treatment arm.

e BCIRG006regimens: doxorubicin and cyclophosphamide followed by docetaxel (AC → T) or docetaxel plus trastuzumab (AC → TH); docetaxel and carboplatin plus trastuzumab (TCH).

Figure 1

NSABP B31 and NCCTG N9831: Cumulative Incidence of Time to First LVEF Decline of ≥ 10 Percentage Points from Baseline and toBelow 50% with Death as a Competing Risk Event

Time 0 is initiation of paclitaxel or trastuzumab + paclitaxel therapy.

Figure 2

HERA: Cumulative Incidence of Time to First LVEF Decline of ≥ 10 Percentage Points from Baseline and to Below 50% with Death as a Competing Risk Event

Time 0 is the date of randomization.

Figure 3

BCIRG006: Cumulative Incidence of Time to First LVEF Decline of ≥ 10 Percentage Points from Baseline and to Below 50% with Death as a Competing Risk Event

Time 0 is the date of randomization.

The incidence of congestive heart failure among patients in the metastatic breast cancer trials was classified for severity using the New York Heart Association classification system (I−IV, where IV is the most severe level of cardiac failure) (see Table 2). In the metastatic breast cancer trials, the probability of cardiac dysfunction was highest in patients who received trastuzumab concurrently with anthracyclines.

In ToGA, 5% of patients in the trastuzumab plus chemotherapy arm compared to 1.1% of patients in the chemotherapy alone arm had LVEF value below 50% with a ≥ 10% absolute decrease in LVEF from pretreatment values.

Infusion Reactions

During the first infusion with trastuzumab, the symptoms most commonly reported were chills and fever, occurring in approximately 40% of patients in clinical trials. Symptoms were treated with acetaminophen, diphenhydramine, and meperidine (with or without reduction in the rate of trastuzumab infusion); permanent discontinuation of trastuzumab for infusion reactions was required in < 1% of patients. Other signs and/or symptoms may include nausea, vomiting, pain (in some cases at tumor sites), rigors, headache, dizziness, dyspnea, hypotension, elevated blood pressure, rash, and asthenia. Infusion reactions occurred in 21% and 35% of patients, and were severe in 1.4% and 9% of patients, on second or subsequent trastuzumab infusions administered as monotherapy or in combination with chemotherapy, respectively. In the post-marketing setting, severe infusion reactions, including hypersensitivity, anaphylaxis, and angioedema have been reported.

Anemia

In randomized controlled clinical trials, the overall incidence of anemia (30% vs. 21% [H0648g]), of selected NCI-CTC Grade 2 to 5 anemia (12.3% vs. 6.7% [NSABP B31]), and of anemia requiring transfusions (0.1% vs. 0 patients [NCCTG N9831]) were increased in patients receiving trastuzumab and chemotherapy compared with those receiving chemotherapy alone. Following the administration of trastuzumab as a single agent (H0649g), the incidence of NCI-CTC Grade 3 anemia was < 1%. In ToGA (metastatic gastric cancer), on the trastuzumab containing arm as compared to the chemotherapy alone arm, the overall incidence of anemia was 28% compared to 21% and of NCICTC Grade 3/4 anemia was 12.2% compared to 10.3%.

Neutropenia

In randomized controlled clinical trials in the adjuvant setting, the incidence of selected NCI-CTC Grade 4 to 5 neutropenia (1.7% vs. 0.8% [NCCTG N9831]) and of selected Grade 2 to 5 neutropenia (6.4% vs. 4.3% [NSABP B31]) were increased in patients receiving trastuzumab and chemotherapy compared with those receiving chemotherapy alone. In a randomized, controlled trial in patients with metastatic breast cancer, the incidences of NCI-CTC Grade 3/4 neutropenia (32% vs. 22%) and of febrile neutropenia (23% vs. 17%) were also increased in patients randomized to trastuzumab in combination with myelosuppressive chemotherapy as compared to chemotherapy alone. In ToGA (metastatic gastric cancer) on the trastuzumab containing arm as compared to the chemotherapy alone arm, the incidence of NCI-CTC Grade 3/4 neutropenia was 36.8% compared to 28.9%; febrile neutropenia 5.1% compared to 2.8%.

Infection

The overall incidences of infection (46% vs. 30% [H0648g]), of selected NCI-CTC Grade 2 to 5 infection/febrile neutropenia (24.3% vs. 13.4% [NSABP B31]) and of selected Grade 3 to 5 infection/febrile neutropenia (2.9% vs. 1.4%) [NCCTG N9831]) were higher in patients receiving trastuzumab and chemotherapy compared with those receiving chemotherapy alone. The most common site of infections in the adjuvant setting involved the upper respiratory tract, skin, and urinary tract.

In BCIRG006, the overall incidence of infection was higher with the addition of trastuzumab to AC-T but not to TCH [44% (AC-TH), 37% (TCH), 38% (AC-T)]. The incidences of NCI-CTC Grade 3 to 4 infection were similar [25% (AC-TH), 21% (TCH), 23% (AC-T)] across the three arms.

In a randomized, controlled trial in treatment of metastatic breast cancer, the reported incidence of febrile neutropenia was higher (23% vs. 17%) in patients receiving trastuzumab in combination with myelosuppressive chemotherapy as compared to chemotherapy alone.

Pulmonary Toxicity

Adjuvant Breast Cancer

Among women receiving adjuvant therapy for breast cancer, the incidence of selected NCI-CTC Grade 2 to 5 pulmonary toxicity (14.3% vs. 5.4% [NSABP B31]) and of selected NCI-CTC Grade 3 to 5 pulmonary toxicity and spontaneous reported Grade 2 dyspnea (3.4 % vs. 0.9% [NCCTG N9831]) was higher in patients receiving trastuzumab and chemotherapy compared with chemotherapy alone.

The most common pulmonary toxicity was dyspnea (NCI-CTC Grade 2 to 5: 11.8% vs. 4.6% [NSABP B31]; NCI-CTC Grade 2 to 5: 2.4% vs. 0.2% [NCCTG N9831]).

Pneumonitis/pulmonary infiltrates occurred in 0.7% of patients receiving trastuzumab compared with 0.3% of those receiving chemotherapy alone. Fatal respiratory failure occurred in 3 patients receiving trastuzumab, one as a component of multi-organ system failure, as compared to 1 patient receiving chemotherapy alone.

In HERA, there were 4 cases of interstitial pneumonitis in the one-year trastuzumab treatment arm compared to none in the observation arm at a median follow-up duration of 12.6 months.

Metastatic Breast Cancer

Among women receiving trastuzumab for treatment of metastatic breast cancer, the incidence of pulmonary toxicity was also increased. Pulmonary adverse events have been reported in the post-marketing experience as part of the symptom complex of infusion reactions. Pulmonary events include bronchospasm, hypoxia, dyspnea, pulmonary infiltrates, pleural effusions, non-cardiogenic pulmonary edema, and acute respiratory distress syndrome. For a detailed description, see Warnings and Precautions (5.4).

Thrombosis/Embolism

In 4 randomized, controlled clinical trials, the incidence of thrombotic adverse events was higher in patients receiving trastuzumab and chemotherapy compared to chemotherapy alone in three studies (2.6% vs. 1.5% [NSABP B31], 2.5% and 3.7% vs. 2.2% [BCIRG006] and 2.1% vs. 0% [H0648g]).

Diarrhea

Among women receiving adjuvant therapy for breast cancer, the incidence of NCI-CTC Grade 2 to 5 diarrhea (6.7% vs. 5.4% [NSABP B31]) and of NCI-CTC Grade 3 to 5 diarrhea (2.2% vs. 0% [NCCTG N9831]), and of Grade 1 to 4 diarrhea (7% vs. 1% [HERA; one-year trastuzumab treatment at 12.6 months median duration of follow-up]) were higher in patients receiving trastuzumab as compared to controls. In BCIRG006, the incidence of Grade 3 to 4 diarrhea was higher [5.7% AC-TH, 5.5% TCH vs. 3.0% AC-T] and of Grade 1 to 4 was higher [51% AC-TH, 63% TCH vs. 43% AC-T] among women receiving trastuzumab. Of patients receiving trastuzumab as a single agent for the treatment of metastatic breast cancer, 25% experienced diarrhea. An increased incidence of diarrhea was observed in patients receiving trastuzumab in combination with chemotherapy for treatment of metastatic breast cancer.

Renal Toxicity

In ToGA (metastatic gastric cancer) on the trastuzumab-containing arm as compared to the chemotherapy alone arm the incidence of renal impairment was 18% compared to 14.5%. Severe (Grade 3/4) renal failure was 2.7% on the trastuzumab-containing arm compared to 1.7% on the chemotherapy only arm. Treatment discontinuation for renal insufficiency/failure was 2% on the trastuzumab-containing arm and 0.3% on the chemotherapy only arm.

In the post-marketing setting, rare cases of nephrotic syndrome with pathologic evidence of glomerulopathy have been reported. The time to onset ranged from 4 months to approximately 18 months from initiation of trastuzumab therapy. Pathologic findings included membranous glomerulonephritis, focal glomerulosclerosis, and fibrillary glomerulonephritis. Complications included volume overload and congestive heart failure.

6.2 Post-Marketing Experience

The following adverse reactions have been identified during post-approval use of trastuzumab products. Because these reactions are reported voluntarily from a population of uncertain size, it is not always possible to reliably estimate their frequency or establish a causal relationship to drug exposure.

- Infusion reaction [see Warnings and Precautions (5.2)]
- Oligohydramnios or oligohydramnios sequence, including pulmonary hypoplasia, skeletal abnormalities, and neonatal death [see Warnings and Precautions (5.3)]
- Glomerulopathy [see Adverse Reactions (6.1)]
- Immune thrombocytopenia
- Tumor lysis syndrome (TLS): Cases of possible TLS have been reported in patients treated with trastuzumab products. Patients with significant tumor burden (e.g. bulky metastases) may be at a higher risk. Patients could present with hyperuricemia, hyperphosphatemia, and acute renal failure which may represent possible TLS. Providers should consider additional monitoring and/or treatment as clinically indicated.

7 DRUG INTERACTIONS

Anthracyclines

Patients who receive anthracycline after stopping trastuzumab products may be at increased risk of cardiac dysfunction because of trastuzumab products estimated long washout period [see Clinical Pharmacology (12.3)]. If possible, avoid anthracycline-based therapy for up to 7 months after stopping trastuzumab products. If anthracyclines are used, closely monitor the patient’s cardiac function.

8 USE IN SPECIFIC POPULATIONS

8.1 Pregnancy

Risk Summary

Trastuzumab products can cause fetal harm when administered to a pregnant woman. In post-marketing reports and published literature, use of trastuzumab products during pregnancy resulted in cases of oligohydramnios and of oligohydramnios sequence, manifesting as pulmonary hypoplasia, skeletal abnormalities, and neonatal death [see Data]. Apprise the patient of the potential risks to a fetus. There are clinical considerations if a trastuzumab product is used in a pregnant woman or if a patient becomes pregnant within 7 months following the last dose of a trastuzumab product [see Clinical Considerations].

The background risk of major birth defects and miscarriage for the indicated population is unknown. In the U.S. general population, the estimated background risk of major birth defects and miscarriage in clinically recognized pregnancies is 2% to 4% and 15% to 20%, respectively.

Clinical Considerations

Fetal/Neonatal Adverse Reactions

Monitor women who received Ogivri during pregnancy or within 7 months prior to conception for oligohydramnios. If oligohydramnios occurs, perform fetal/neonatal testing that is appropriate for gestational age and consistent with community standards of care.

Data

Human Data

In post-marketing reports and published literature, use of trastuzumab products during pregnancy resulted in cases of oligohydramnios and of oligohydramnios sequence. Fetal manifestations includedpulmonary hypoplasia, skeletal abnormalities and neonatal death. These case reports described oligohydramnios in pregnant women who received trastuzumab either alone or in combination with chemotherapy. In most reported cases, amniotic fluid index increased after trastuzumab was stopped. In reported cases where trastuzumab therapy was resumed after amniotic index improved, oligohydramnios recurred.

Animal Data

In studies where trastuzumab was administered to pregnant Cynomolgus monkeys during the period of organogenesis at doses up to 25 mg/kg given twice weekly (up to 25 times the recommended weekly human dose of 2 mg/kg), trastuzumab crossed the placental barrier during the early (Gestation Days 20 to 50) and late (Gestation Days 120 to 150) phases of gestation. The resulting concentrations of trastuzumab in fetal serum and amniotic fluid were approximately 33% and 25%, respectively, of those present in the maternal serum but were not associated with adverse developmental effects.

8.2 Lactation

Risk Summary

There is no information regarding the presence of trastuzumab products in human milk, the effects on the breastfed infant, or the effects on milk production. Published data suggest human IgG is present in human milk but does not enter the neonatal and infant circulation in substantial amounts. Trastuzumab was present in the milk of lactating Cynomolgus monkeys but not associated with neonatal toxicity (see Data). Consider the developmental and health benefits of breastfeeding along with the mother’s clinical need for Ogivri treatment and any potential adverse effects on the breastfed child from Ogivri or from the underlying maternal condition. This consideration should also take into account the trastuzumab product wash out period of 7 months [see Clinical Pharmacology (12.3)].

Data

In lactating Cynomolgus monkeys, trastuzumab was present in breast milk at about 0.3% of maternal serum concentrations after pre-(beginning Gestation Day 120) and post-partum (through Post-partum Day 28) doses of 25 mg/kg administered twice weekly (25 times the recommended weekly human dose of 2 mg/kg of trastuzumab products). Infant monkeys with detectable serum levels of trastuzumab did not exhibit any adverse effects on growth or development from birth to 1 month of age.

8.3 Females and Males of Reproductive Potential

Pregnancy Testing

Verify the pregnancy status of females of reproductive potential prior to the initiation of Ogivri.

Contraception

Females

Trastuzumab products can cause embryo-fetal harm when administered during pregnancy. Advise females of reproductive potential to use effective contraception during treatment with Ogivri and for 7 months following the last dose of Ogivri [see Use in Specific Populations (8.1) and Clinical Pharmacology (12.3)].

8.4 Pediatric Use

The safety and effectiveness of Ogivri in pediatric patients have not been established.

8.5 Geriatric Use

Trastuzumab has been administered to 386 patients who were 65 years of age or over (253 in the adjuvant treatment and 133 in metastatic breast cancer treatment settings). The risk of cardiac dysfunction was increased in geriatric patients as compared to younger patients in both those receiving treatment for metastatic disease in Studies H0648g and H0649g, or adjuvant therapy in Studies NSABP B31 and NCCTG N9831. Limitations in data collection and differences in study design of the 4 studies of trastuzumab in adjuvant treatment of breast cancer preclude a determination of whether the toxicity profile of trastuzumab in older patients is different from younger patients. The reported clinical experience is not adequate to determine whether the efficacy improvements (ORR, TTP, OS, DFS) of trastuzumab treatment in older patients is different from that observed in patients < 65 years of age for metastatic disease and adjuvant treatment.

In ToGA (metastatic gastric cancer), of the 294 patients treated with trastuzumab, 108 (37%) were 65 years of age or older, while 13 (4.4%) were 75 and over. No overall differences in safety or effectiveness were observed.

11 DESCRIPTION

Trastuzumab-dkst is a humanized IgG1 kappa monoclonal antibody that selectively binds with high affinity to the extracellular domain of the human epidermal growth factor receptor 2 protein, HER2. Trastuzumab-dkst is produced by recombinant DNA technology in a mammalian cell (Chinese Hamster Ovary) culture.

Ogivri (trastuzumab-dkst) for injection is a sterile, off-white to pale yellow, preservative-free lyophilized powder with a cake-like appearance, for injection, for intravenous administration.

Each multiple-dose vial of Ogivri delivers 420 mg trastuzumab-dkst, D-sorbitol (322.6 mg), L-Histidine (6.0 mg), Histidine hydrochloride monohydrate (9.4 mg) and Polyethylene glycol 3350/Macrogol 3350 (94.1 mg). Hydrochloric acid or sodium hydroxide may be used to adjust the pH of the formulation buffer. Reconstitution with 20 mL of the appropriate diluent (BWFI or SWFI) yields a solution containing 21 mg/mL trastuzumab-dkst that delivers 20 mL (420 mg trastuzumab-dkst), at a pH of approximately 6. If Ogivri is reconstituted with SWFI without preservative, the reconstituted solution is considered single-dose.

Each single-dose vial of Ogivri delivers 150 mg trastuzumab-dkst, D-sorbitol (115.2 mg), L-Histidine (2.16 mg), L-Histidine hydrochloride monohydrate (3.36 mg) and Polyethylene glycol 3350/Macrogol 3350 (33.6 mg). Hydrochloric acid or sodium hydroxide may be used to adjust the pH of the formulation buffer. Reconstitution with 7.4 mL of sterile water for injection (SWFI) yields a solution containing 21 mg/mL trastuzumab-dkst that delivers 7.15 mL (150 mg trastuzumab-dkst), at a pH of approximately 6.

12 CLINICAL PHARMACOLOGY

12.1 Mechanism of Action

The HER2 (or c-erbB2) proto-oncogene encodes a transmembrane receptor protein of 185 kDa, which is structurally related to the epidermal growth factor receptor. Trastuzumab products have been shown, in both in vitro assays and in animals, to inhibit the proliferation of human tumor cells that overexpress HER2.

Trastuzumab products are mediators of antibody-dependent cellular cytotoxicity (ADCC). In vitro, trastuzumab product-mediated ADCC has been shown to be preferentially exerted on HER2 overexpressing cancer cells compared with cancer cells that do not overexpress HER2.

12.2 Pharmacodynamics

Trastuzumab product exposure-response relationships and the time course of pharmacodynamic responses are not fully characterized.

Cardiac Electrophysiology

The effects of trastuzumab on electrocardiographic (ECG) endpoints, including QTc interval duration, were evaluated in patients with HER2 positive solid tumors. Trastuzumab had no clinically relevant effect on the QTc interval duration and there was no apparent relationship between serum trastuzumab concentrations and change in QTcF interval duration in patients with HER2 positive solid tumors.

12.3 Pharmacokinetics

The pharmacokinetics of trastuzumab were evaluated in a pooled population pharmacokinetic (PK) model analysis of 1,582 subjects with primarily breast cancer and metastatic gastric cancer (MGC) receiving intravenous trastuzumab. Total trastuzumab clearance increases with decreasing concentrations due to parallel linear and non-linear elimination pathways.

Although the average trastuzumab exposure was higher following the first cycle in breast cancer patients receiving the once every three week schedule compared to the weekly schedule of trastuzumab, the average steady-state exposure was essentially the same at both dosages. The average trastuzumab exposure following the first cycle and at steady state as well as the time to steady state was higher in breast cancer patients compared to MGC patients at the same dosage; however, the reason for this exposure difference is unknown. Additional predicted trastuzumab exposure and PK parameters following the first trastuzumab cycle and at steady state exposure are described in Tables 7 and 8, respectively.

Population PK based simulations indicate that following discontinuation of trastuzumab, concentrations in at least 95% of breast cancer patients and MGC patients will decrease to approximately 3% of the population predicted steady-state trough serum concentration (approximately 97% washout) by 7 months [see Warnings and Precautions (5.1) and Use in Specific Populations (8.1, 8.3)].

Table 7

Population Predicted Cycle 1 PK Exposures (Median with 5th to 95th Percentiles) in Breast Cancer

and MGC Patients

Schedule | Primary tumor; type | N | Cmin; (µg/mL) | Cmax; (µg/mL) | AUC0-21days; (µg.day/mL)
8 mg/kg +; 6 mg/kg q3w | Breast cancer | 1195 | 29.4; (5.8 to 59.5) | 178; (117 to 291) | 1373; (736 to 2245)
8 mg/kg +; 6 mg/kg q3w | MGC | 274 | 23.1; (6.1 to50.3) | 132; (84.2 to 225) | 1109; (588 to 1938)
4 mg/kg +; 2 mg/kg qw | Breast cancer | 1195 | 37.7; (12.3 to 70.9) | 88.3; (58 to 144) | 1066; (586 to 1754)

Table 8

Population Predicted Steady State PK Exposures (Median with 5th to 95th Percentiles) in Breast

Cancer and MGC Patients

Schedule | Primary tumor type | N | Cmin,ssa; (µg/mL) | Cmax,ssb; (µg/mL) | AUCss,0-21days; (µg.day/mL) | Time to steady-state (week) | Total CL range at steady-state (L/day)
8 mg/kg +; 6 mg/kg; q3w | Breast; cancer | 1195 | 47.4; (5 to 115) | 179; (107 to 309) | 1794; (673 to 3618) | 12 | 0.173 to 0.283
8 mg/kg +; 6 mg/kg; q3w | MGC | 274 | 32.9; (6.1 to 88.9) | 131; (72.5 to 251) | 1338; (557 to 2875) | 9 | 0.189 to 0.337
4 mg/kg +; 2 mg/kg qw | Breast; cancer | 1195 | 66.1; (14.9 to 142) | 109; (51.0 to 209) | 1765; (647 to 3578) | 12 | 0.201 to 0.244

a Steady-state trough serum concentration of trastuzumab

b Maximum steady-state serum concentration of trastuzumab

Specific Populations

Based on a population pharmacokinetic analysis, no clinically significant differences were observed in the pharmacokinetics of trastuzumab based on age (<65 (n = 1294); ≥65 (n = 288)), race (Asian (n = 264); non-Asian (n = 1324)) and renal impairment (mild (creatinine clearance [CLcr] 60 to 90 mL/min) (n = 636) or moderate (CLcr 30 to 60 mL/min) (n = 133)). The pharmacokinetics of trastuzumab products in patients with severe renal impairment, end-stage renal disease with or without hemodialysis, or hepatic impairment is unknown.

Drug Interaction Studies

There have been no formal drug interaction studies performed with trastuzumab products in humans. Clinically significant interactions between trastuzumab and concomitant medications used in clinical trials have not been observed.

Paclitaxel and doxorubicin: Concentrations of paclitaxel and doxorubicin and their major metabolites (i.e., 6-α hydroxyl-paclitaxel [POH], and doxorubicinol [DOL], respectively) were not altered in the presence of trastuzumab when used as combination therapy in clinical trials. Trastuzumab concentrations were not altered as part of this combination therapy.

Docetaxel and carboplatin: When trastuzumab was administered in combination with docetaxel or carboplatin, neither the plasma concentrations of docetaxel or carboplatin nor the plasma concentrations of trastuzumab were altered.

Cisplatin and capecitabine: In a drug interaction substudy conducted in patients in ToGA, the pharmacokinetics of cisplatin, capecitabine and their metabolites were not altered when administered in combination with trastuzumab.

12.6 Immunogenicity

The observed incidence of anti-drug antibodies is highly dependent on the sensitivity and specificity of the assay. Differences in assay methods preclude meaningful comparisons of the incidence of anti-drug antibodies in the studies described below with the incidence of anti-drug antibodies in other studies, including those of trastuzumab or of other trastuzumab products.

Among 903 women with metastatic breast cancer, human anti human antibody (HAHA) to trastuzumab was detected in one patient using an enzyme linked immunosorbent assay (ELISA). This patient did not experience an allergic reaction. Samples for assessment of HAHA were not collected in studies of adjuvant breast cancer.

The clinical relevance of the development of anti-trastuzumab antibodies after treatment with trastuzumab is not known.

13 NONCLINICAL TOXICOLOGY

13.1 Carcinogenesis, Mutagenesis, Impairment of Fertility

Trastuzumab products have not been tested for carcinogenic potential.

No evidence of mutagenic activity was observed when trastuzumab was tested in the standard Ames bacterial and human peripheral blood lymphocyte mutagenicity assays, at concentrations of up to 5000 mcg/mL. In an in vivo micronucleus assay, no evidence of chromosomal damage to mouse bone marrow cells was observed following bolus intravenous doses of up to 118 mg/kg of trastuzumab.

A fertility study was conducted in female cynomolgus monkeys at doses up to 25 times the weekly recommended human dose of 2 mg/kg of trastuzumab and has revealed no evidence of impaired fertility, as measured by menstrual cycle duration and female sex hormone levels.

14 CLINICAL STUDIES

14.1 Adjuvant Breast Cancer

The safety and efficacy of trastuzumab in women receiving adjuvant chemotherapy for HER2 overexpressing breast cancer were evaluated in an integrated analysis of two randomized, open-label, clinical trials (Studies NSABP B31 and NCCTG N9831) with a total of 4063 women at the protocol-specified final overall survival analysis, a third randomized, open-label, clinical trial (HERA) with a total of 3386 women at definitive Disease-Free Survival analysis for one-year trastuzumab treatment versus observation, and a fourth randomized, open-label clinical trial with a total of 3222 patients (BCIRG006).

NSABP B31 and NCCTG N9831

In NSABP B31 and NCCTG N9831, breast tumor specimens were required to show HER2 overexpression (3+ by IHC) or gene amplification (by FISH). HER2 testing was verified by a central laboratory prior to randomization (NCCTG N9831) or was required to be performed at a reference laboratory (NSABP B31). Patients with a history of active cardiac disease based on symptoms, abnormal electrocardiographic, radiologic, or left ventricular ejection fraction findings or uncontrolled hypertension (diastolic > 100 mm Hg or systolic > 200 mm Hg) were not eligible.

Patients were randomized (1:1) to receive doxorubicin and cyclophosphamide followed by paclitaxel (AC → paclitaxel) alone or paclitaxel plus trastuzumab (AC → paclitaxel + trastuzumab). In both trials, patients received four 21-day cycles of doxorubicin 60 mg/m^2 and cyclophosphamide 600 mg/m^2. Paclitaxel was administered either weekly (80 mg/m^2) or every 3 weeks (175 mg/m^2) for a total of 12 weeks in NSABP B31; paclitaxel was administered only by the weekly schedule in NCCTG N9831. Trastuzumab was administered at 4 mg/kg on the day of initiation of paclitaxel and then at a dose of 2 mg/kg weekly for a total of 52 weeks. Trastuzumab treatment was permanently discontinued in patients who developed congestive heart failure, or persistent/recurrent LVEF decline [see Dosage and Administration (2.5)]. Radiation therapy, if administered, was initiated after the completion of chemotherapy. Patients with ER+ and/or PR+ tumors received hormonal therapy. The major efficacy outcome measure of the combined efficacy analysis was Disease-Free Survival (DFS), defined as the time from randomization to recurrence, occurrence of contralateral breast cancer, other second primary cancer, or death. An additional efficacy outcome measure was overall survival (OS).

A total of 3752 patients were included in the joint efficacy analysis of DFS following a median follow-up of 2.0 years in the AC → paclitaxel + trastuzumab arm. The pre-planned final OS analysis from the joint analysis included 4063 patients and was performed when 707 deaths had occurred after a median follow-up of 8.3 years in the AC → paclitaxel + trastuzumab arm. The data from both arms in NSABP B31 and two of the three study arms in NCCTG N9831 were pooled for efficacy analyses.

The patients included in the DFS analysis had a median age of 49 years (range, 22 to 80 years; 6% > 65 years), 84% were white, 7% black, 4% Hispanic, and 4% Asian/Pacific Islander. Disease characteristics included 90% infiltrating ductal histology, 38% T1, 91% nodal involvement, 27% intermediate and 66% high grade pathology, and 53% ER+ and/or PR+ tumors.

HERA

In HERA, breast tumor specimens were required to show HER2 overexpression (3+ by IHC) or gene amplification (by FISH) as determined at a central laboratory. Patients with node-negative disease were required to have ≥ T1c primary tumor. Patients with a history of congestive heart failure or LVEF < 55%, uncontrolled arrhythmias, angina requiring medication, clinically significant valvular heart disease, evidence of transmural infarction on ECG, poorly controlled hypertension (systolic > 180 mm Hg or diastolic > 100 mm Hg) were not eligible.

Patients were randomized (1:1:1) upon completion of definitive surgery, and at least four cycles of chemotherapy to receive no additional treatment, or one year of trastuzumab treatment or two years of trastuzumab treatment. Patients undergoing a lumpectomy had also completed standard radiotherapy. Patients with ER+ and/or PgR+ disease received systemic adjuvant hormonal therapy at investigator discretion. Trastuzumab was administered with an initial dose of 8 mg/kg followed by subsequent doses of 6 mg/kg once every three weeks. The major efficacy outcome measure was Disease-Free Survival (DFS), defined as in NSABP B31 and NCCTG N9831.

HERA was designed to compare one and two years of once every three week trastuzumab treatment versus observation in patients with HER2 positive EBC following surgery, established chemotherapy and radiotherapy (if applicable). A protocol specified interim efficacy analysis comparing one-year trastuzumab treatment to observation was performed at a median follow-up duration of 12.6 months in the trastuzumab arm.

Among the 3386 patients randomized to the observation (n = 1693) and trastuzumab one-year (n = 1693) treatment arms, the median age was 49 years (range 21 to 80), 83% were White, and 13% were Asian. Disease characteristics: 94% infiltrating ductal carcinoma, 50% ER+ and/or PgR+, 57% node positive, 32% node negative, and in 11% of patients, nodal status was not assessable due to prior neo-adjuvant chemotherapy. Ninety-six percent (1055/1098) of patients with node-negative disease had high-risk features: among the 1098 patients with node-negative disease, 49% (543) were ER− and PgR−, and 47% (512) were ER and/or PgR + and had at least one of the following high-risk features: pathological tumor size greater than 2 cm, Grade 2 to 3, or age <35 years. Prior to randomization, 94% of patients had received anthracycline-based chemotherapy regimens.

After the DFS results comparing observation to one-year trastuzumab treatment were disclosed, a prospectively planned analysis that included comparison of one year versus two years of trastuzumab treatment at a median follow-up duration of 8 years was performed. Based on this analysis, extending trastuzumab treatment for a duration of two years did not show additional benefit over treatment for one year [Hazard Ratios of two-years trastuzumab versus one-year trastuzumab treatment in the intent to treat (ITT) population for Disease-Free Survival (DFS) = 0.99 (95% CI: 0.87, 1.13), p-value = 0.90 and Overall Survival (OS) = 0.98 (0.83, 1.15); p-value = 0.78].

BCIRG006

In BCIRG006, breast tumor specimens were required to show HER2 gene amplification (FISH+ only) as determined at a central laboratory. Patients were required to have either node-positive disease, or node-negative disease with at least one of the following high-risk features: ER/PR-negative, tumor size > 2 cm, age < 35 years, or histologic and/or nuclear Grade 2 or 3. Patients with a history of CHF, myocardial infarction, Grade 3 or 4 cardiac arrhythmia, angina requiring medication, clinically significant valvular heart disease, poorly controlled hypertension (diastolic > 100 mm Hg), any T4 or N2 or known N3 or M1 breast cancer were not eligible.

Patients were randomized (1:1:1) to receive doxorubicin and cyclophosphamide followed by docetaxel (AC-T), doxorubicin and cyclophosphamide followed by docetaxel plus trastuzumab (AC-TH), or docetaxel and carboplatin plus trastuzumab (TCH). In both the AC-T and AC-TH arms, doxorubicin 60 mg/m^2 and cyclophosphamide 600 mg/m^2 were administered every 3 weeks for four cycles; docetaxel 100 mg/m^2 was administered every 3 weeks for four cycles. In the TCH arm, docetaxel 75 mg/m^2 and carboplatin (at a target AUC of 6 mg/mL/min as a 30-to 60-minute infusion) were administered every 3 weeks for six cycles. Trastuzumab was administered weekly (initial dose of 4 mg/kg followed by weekly dose of 2 mg/kg) concurrently with either T or TC, and then every 3 weeks (6 mg/kg) as monotherapy for a total of 52 weeks. Radiation therapy, if administered, was initiated after completion of chemotherapy. Patients with ER+ and/or PR+ tumors received hormonal therapy. Disease-Free Survival (DFS) was the major efficacy outcome measure.

Among 3222 patients, the median age was 49 (range 22 to 74 years; 6% ≥ 65 years). Disease characteristics included 54% ER+ and/or PR+ and 71% node positive. Prior to randomization, all patients underwent primary surgery for breast cancer.

The results for DFS for the integrated analysis of NSABP B31 and NCCTG N9831, HERA, and BCIRG006 and OS results for the integrated analysis of NSABP B31 and NCCTG N9831, and HERA are presented in Table 9. For NSABP B31 and NCCTG N9831, the duration of DFS following a median follow-up of 2.0 years in the AC → TH arm is presented in Figure 4, and the duration of OS after a median follow-up of 8.3 years in the AC → TH arm is presented in Figure 5. The duration of DFS for BCIRG006is presented in Figure 6. For NSABP B31 and NCCTG N9831, the OS hazard ratio was 0.64 (95% CI: 0.55, 0.74). At 8.3 years of median follow-up [AC → TH], the survival rate was estimated to be 86.9% in the AC → TH arm and 79.4% in the AC → T arm. The final OS analysis results from NSABP B31 and NCCTG N9831 indicate that OS benefit by age, hormone receptor status, number of positive lymph nodes, tumor size and grade, and surgery/radiation therapy was consistent with the treatment effect in the overall population. In patients ≤ 50 years of age (n = 2197), the OS hazard ratio was 0.65 (95% CI: 0.52, 0.81) and in patients > 50 years of age (n = 1866), the OS hazard ratio was 0.63 (95% CI: 0.51, 0.78). In the subgroup of patients with hormone receptor-positive disease (ER-positive and/or PR-positive) (n = 2223), the hazard ratio for OS was 0.63 (95% CI: 0.51, 0.78). In the subgroup of patients with hormone receptor-negative disease (ER-negative and PR-negative) (n = 1830), the hazard ratio for OS was 0.64 (95% CI: 0.52, 0.80). In the subgroup of patients with tumor size ≤ 2 cm (n = 1604), the hazard ratio for OS was 0.52 (95% CI: 0.39, 0.71). In the subgroup of patients with tumor size > 2 cm (n = 2448), the hazard ratio for OS was 0.67 (95% CI: 0.56, 0.80).

Table 9

Efficacy Results from Adjuvant Treatment of Breast Cancer (NSABP B31 and NCCTG N9831, HERA, and BCIRG006)

 | DFS; events | DFS Hazard; ratio; (95% CI); p-value | Deaths; (OS events) | OS Hazard; ratio; p-value
NSABP B31 and NCCTG N9831a
AC → TH; (n = 1872)b; (n = 2031)c | 133b | 0.48b,d; (0.39, 0.59); p < 0.0001e | 289c | 0.64c,d; (0.55, 0.74); p < 0.0001e
AC → T; (n = 1880)b; (n = 2032)c | 261b |  | 418c
HERAf
Chemo →; Trastuzumab; (n = 1693) | 127 | 0.54; (0.44, 0.67); p < 0.0001g | 31 | 0.75; p = NSh
Chemo →; Observation; (n = 1693) | 219 |  | 40
BCIRG006i
TCH; (n = 1075) | 134 | 0.67; (0.54 to 0.84); p = 0.0006e,j | 56
AC → TH; (n = 1074) | 121 | 0.60; (0.48 to 0.76); p < 0.0001e,i | 49
AC → T; (n = 1073) | 180 |  | 80

CI = confidence interval.

a NSABP B31 and NCCTG N9831 regimens: doxorubicin and cyclophosphamide followed by paclitaxel (AC → T) or paclitaxel plus trastuzumab (AC → TH).

b Efficacy evaluable population, for the primary DFS analysis, following a median follow-up of 2.0 years in the AC → TH arm.

c Efficacy evaluable population, for the final OS analysis, following 707 deaths (8.3 years of median follow-up in the AC → TH arm).

d Hazard ratio estimated by Cox regression stratified by clinical trial, intended paclitaxel schedule, number of positive nodes, and hormone receptor status.

e stratified log-rank test.

f At definitive DFS analysis with median duration of follow-up of 12.6 months in the one-year trastuzumab treatment arm.

g log-rank test.

h NS = non-significant.

i BCIRG006 regimens: doxorubicin and cyclophosphamide followed by docetaxel (AC → T) or docetaxel plus trastuzumab (AC → TH); docetaxel and carboplatin plus trastuzumab (TCH).

j A two-sided alpha level of 0.025 for each comparison.

Figure 4

Duration of Disease-Free Survival in Patients with Adjuvant Treatment of Breast Cancer (NSABP B31 and NCCTG N9831)

Figure 5

Overall Survival in Patients with Adjuvant Treatment of Breast Cancer (NSABP B31 and NCCTG N9831)

Figure 6

Disease-Free Survival in Patients with Adjuvant Treatment of Breast Cancer (BCIRG006)

Exploratory analyses of DFS as a function of HER2 overexpression or gene amplification were conducted for patients in NCCTG N9831 and HERA, where central laboratory testing data were available. The results are shown in Table 10. The number of events in NCCTG N9831 was small with the exception of the IHC 3+/FISH+ subgroup, which constituted 81% of those with data. Definitive conclusions cannot be drawn regarding efficacy within other subgroups due to the small number of events. The number of events in HERA was adequate to demonstrate significant effects on DFS in the IHC 3+/FISH unknown and the FISH +/IHC unknown subgroups.

Table 10: DFS in NCCTG N9831 and HERA for Patients with HER2 Overexpression or Amplification

 | NCCTG N9831 |  | HERAc
HER2 Assay; Resulta | Number of; Patients | Hazard Ratio DFS; (95% CI) | Number of; Patients | Hazard Ratio DFS; (95% CI)
IHC 3+
FISH (+) | 1170 | 0.42; (0.27, 0.64) | 91 | 0.56; (0.13, 2.50)
FISH (–) | 51 | 0.71; (0.04, 11.79) | 8 | —
FISH Unknown | 51 | 0.69; (0.09, 5.14) | 2258 | 0.53; (0.41, 0.69)
IHC < 3+ /; FISH (+) | 174 | 1.01; (0.18, 5.65) | 299b | 0.53; (0.20, 1.42)
IHC unknown /; FISH (+) | — | — | 724 | 0.59; (0.38, 0.93)

a IHC by HercepTest, FISH by PathVysion (HER2/CEP17 ratio ≥ 2.0) as performed at a central laboratory.

b All cases in this category in HERA were IHC 2+.

c Median follow-up duration of 12.6 months in the one-year trastuzumab treatment arm.

14.2 Metastatic Breast Cancer

The safety and efficacy of trastuzumab in treatment of women with metastatic breast cancer were studied in a randomized, controlled clinical trial in combination with chemotherapy (H0648g, n = 469 patients) and an open-label single agent clinical trial (H0649g, n = 222 patients). Both trials studied patients with metastatic breast cancer whose tumors overexpress the HER2 protein. Patients were eligible if they had 2 or 3 levels of overexpression (based on a 0 to 3 scale) by immunohistochemical assessment of tumor tissue performed by a central testing lab.

Previously Untreated Metastatic Breast Cancer (H0648g)

H0648g was a multicenter, randomized, open-label clinical trial conducted in 469 women with metastatic breast cancer who had not been previously treated with chemotherapy for metastatic disease. Tumor specimens were tested by IHC (Clinical Trial Assay, CTA) and scored as 0, 1+, 2+, or 3+, with 3+ indicating the strongest positivity. Only patients with 2+ or 3+ positive tumors were eligible (about 33% of those screened). Patients were randomized to receive chemotherapy alone or in combination with trastuzumab given intravenously as a 4 mg/kg loading dose followed by weekly doses of trastuzumab at 2 mg/kg. For those who had received prior anthracycline therapy in the adjuvant setting, chemotherapy consisted of paclitaxel (175 mg/m^2 over 3 hours every 21 days for at least six cycles); for all other patients, chemotherapy consisted of anthracycline plus cyclophosphamide (AC: doxorubicin 60 mg/m^2 or epirubicin 75 mg/m^2 plus 600 mg/m^2 cyclophosphamide every 21 days for six cycles). Sixty-five percent of patients randomized to receive chemotherapy alone in this study received trastuzumab at the time of disease progression as part of a separate extension study.

Based upon the determination by an independent Response Evaluation Committee the patients randomized to trastuzumab and chemotherapy experienced a significantly longer median time to disease progression (TTP), a higher overall response rate (ORR), and a longer median duration of response (DoR), as compared with patients randomized to chemotherapy alone. Patients randomized to trastuzumab and chemotherapy also had a longer median overall survival (OS) (see Table 11).

These treatment effects were observed both in patients who received trastuzumab plus paclitaxel and in those who received trastuzumab plus AC; however the magnitude of the effects was greater in the paclitaxel subgroup.

Table 11

H0648g: Efficacy Results inFirst-Line Treatment for Metastatic Breast Cancer

 | Combined Results |  | Paclitaxel Subgroup |  | ACa Subgroup
 | trastuzumab +; All Chemo-; therapy; (n = 235) | All Chemo-; therapy; (n = 234) | trastuzumab +; Paclitaxel; (n = 92) | Paclitaxel; (n = 96) | trastuzumab +; ACa; (n = 143) | ACa; (n = 138)
Time to Disease Progression (TTP)
Median; (months)b,c | 7.2 | 4.5 | 6.7 | 2.5 | 7.6 | 5.7
95% CI | 7, 8 | 4, 5 | 5, 10 | 2, 4 | 7, 9 | 5, 7
p-valued | < 0.0001 |  | < 0.0001 |  | 0.002
Overall Response Rate (ORR)b
Events (n) | 45 | 29 | 38 | 15 | 50 | 38
95% CI | 39, 51 | 23, 35 | 28, 48 | 8, 22 | 42, 58 | 30, 46
p-valuee | < 0.001 |  | < 0.001 |  | 0.10
Duration of Response (DoR)
Median (months)b,c | 8.3 | 5.8 | 8.3 | 4.3 | 8.4 | 6.4
25%, 75%; Quartile | 6, 15 | 4, 8 | 5, 11 | 4, 7 | 6, 15 | 4, 8
Overall Survival (OS)
Median (months)c | 25.1 | 20.3 | 22.1 | 18.4 | 26.8 | 21.4
95% CI | 22, 30 | 17, 24 | 17, 29 | 13, 24 | 23, 33 | 18, 27
p-valued | 0.05 |  | 0.17 |  | 0.16

a AC = Anthracycline (doxorubicin or epirubicin) and cyclophosphamide.

b Assessed by an independent Response Evaluation Committee.

c Kaplan-Meier Estimate.

d log-rank test.

e χ2-test.

Data from H0648g suggest that the beneficial treatment effects were largely limited to patients with the highest level of HER2 protein overexpression (3+) (see Table 12).

Table 12

Treatment Effects in H0648g as a Function of HER2 Overexpression or Amplification

HER2 Assay; Result | Number of; Patients; (N) | Relative Riskb for Time to; Disease Progression; (95% CI) | Relative Riskb for; Mortality; (95% CI)
CTA 2+ or 3+ | 469 | 0.49 (0.40, 0.61) | 0.80 (0.64, 1.00)
FISH (+)a | 325 | 0.44 (0.34, 0.57) | 0.70 (0.53, 0.91)
FISH (−)a | 126 | 0.62 (0.42, 0.94) | 1.06 (0.70, 1.63)
CTA 2+ | 120 | 0.76 (0.50, 1.15) | 1.26 (0.82, 1.94)
FISH (+) | 32 | 0.54 (0.21, 1.35) | 1.31 (0.53, 3.27)
FISH (−) | 83 | 0.77 (0.48, 1.25) | 1.11 (0.68, 1.82)
CTA 3+ | 349 | 0.42 (0.33, 0.54) | 0.70 (0.51, 0.90)
FISH (+) | 293 | 0.42 (0.32, 0.55) | 0.67 (0.51, 0.89)
FISH (−) | 43 | 0.43 (0.20, 0.94) | 0.88 (0.39, 1.98)

a FISH testing results were available for 451 of the 469 patients enrolled on study.

b The relative risk represents the risk of progression or death in the trastuzumab plus chemotherapy arm versus the chemotherapy arm.

Previously Treated Metastatic Breast Cancer (H0649g)

Trastuzumab was studied as a single agent in a multicenter, open-label, single-arm clinical trial (H0649g) in patients with HER2 overexpressing metastatic breast cancer who had relapsed following one or two prior chemotherapy regimens for metastatic disease. Of 222 patients enrolled, 66% had received prior adjuvant chemotherapy, 68% had received two prior chemotherapy regimens for metastatic disease, and 25% had received prior myeloablative treatment with hematopoietic rescue. Patients were treated with a loading dose of 4 mg/kg IV followed by weekly doses of trastuzumab at 2 mg/kg IV.

The ORR (complete response + partial response), as determined by an independent Response Evaluation Committee, was 14%, with a 2% complete response rate and a 12% partial response rate. Complete responses were observed only in patients with disease limited to skin and lymph nodes.

The overall response rate in patients whose tumors tested as CTA 3+ was 18% while in those that tested as CTA 2+, it was 6%.

14.3 Metastatic Gastric Cancer

The safety and efficacy of trastuzumab in combination with cisplatin and a fluoropyrimidine (capecitabine or 5-fluorouracil) were studied in patients previously untreated for metastatic gastric or gastroesophageal junction adenocarcinoma (ToGA). In this open-label, multi-center trial, 594 patients were randomized 1:1 to trastuzumab in combination with cisplatin and a fluoropyrimidine (FC+H) or chemotherapy alone (FC). Randomization was stratified by extent of disease (metastatic vs. locally advanced), primary site (gastric vs. gastroesophageal junction), tumor measurability (yes vs. no), ECOG performance status (0,1 vs. 2), and fluoropyrimidine (capecitabine vs. 5-fluorouracil). All patients were either HER2 gene amplified (FISH+) or HER2 overexpressing (IHC 3+). Patients were also required to have adequate cardiac function (e.g., LVEF > 50%).

On the trastuzumab-containing arm, trastuzumab was administered as an IV infusion at an initial dose of 8 mg/kg followed by 6 mg/kg every 3 weeks until disease progression. On both study arms cisplatin was administered at a dose of 80 mg/m^2 Day 1 every 3 weeks for 6 cycles as a 2 hour IV infusion. On both study arms capecitabine was administered at 1000 mg/m^2 dose orally twice daily (total daily dose 2000 mg/m^2) for 14 days of each 21 day cycle for 6 cycles. Alternatively, continuous intravenous infusion (CIV) 5-fluorouracil was administered at a dose of 800 mg/m^2/day from Day 1 through Day 5 every three weeks for 6 cycles.

The median age of the study population was 60 years (range: 21 to 83); 76% were male; 53% were Asian, 38% Caucasian, 5% Hispanic, 5% other racial/ethnic groups; 91% had ECOG PS of 0 or 1; 82% had primary gastric cancer and 18% had primary gastroesophageal adenocarcinoma. Of these patients, 23% had undergone prior gastrectomy, 7% had received prior neoadjuvant and/or adjuvant therapy, and 2% had received prior radiotherapy.

The main outcome measure of ToGA was overall survival (OS), analyzed by the unstratified logrank test. The final OS analysis based on 351 deaths was statistically significant (nominal significance level of 0.0193). An updated OS analysis was conducted at one year after the final analysis. The efficacy results of both the final and the updated analyses are summarized in Table 13 and Figure 7.

Table 13: Overall Survival in ToGA (ITT Population)
 | FCa + Trastuzumab Arm; N = 298 | FCa Arm; N = 296
Overall Survival (interim analysis)
N (%); Median (months); 95% CI | 167 (56.0%); 13.5; (11.7, 15.7) | 184 (62.2%); 11.0; (9.4, 12.5)
Hazard Ratio; 95% CI; p-valueb | 0.73; (0.60, 0.91); 0.0038
Overall Survival (updated)
N (%); Median (months); 95% CI | 221 (74.2%); 13.1; (11.9, 15.1) | 227 (76.7%); 11.7; (10.3, 13.0)
Hazard Ratio; 95% CI | 0.80; (0.67, 0.97)
a FC = capecitabine vs. 5-fluorouracil
b Two sided p-value comparing with the nominal significance level of 0.0193.

Figure 7

Updated Overall Survival in Patients with Metastatic Gastric Cancer (ToGA)

An exploratory analysis of OS in patients based on HER2 gene amplification (FISH) and protein overexpression (IHC) testing is summarized in Table 14.

Table 14

Exploratory Analyses by HER2 Status Using Updated Overall survival Results

 | FC; (N = 296)a |  | FC + H; (N = 298)b
FISH+ / IHC 0, 1+ subgroup (N = 133)
No. Deaths (%) / n (%) | 57/71 (80%) |  | 56/62 (90%)
Median OS Duration (mos.) | 8.8 |  | 8.3
95% CI (mos.) | (6.4, 11.7) |  | (6.2, 10.7)
Hazard Ratio (95% CI) |  | 1.33 (0.92, 1.92)
FISH+ / IHC2+ subgroup (N = 160)
No. Deaths (%) / n (%) | 65/80 (81%) |  | 64/80 (80%)
Median OS Duration (mos.) | 10.8 |  | 12.3
95% CI (mos.) | (6.8, 12.8) |  | (9.5, 15.7)
Hazard Ratio (95% CI) |  | 0.78 (0.55, 1.10)
FISH+ or FISH-/ IHC3+c subgroup (N = 294)
No. Deaths (%) / n (%) | 104/143 (73%) |  | 96/151 (64%)
Median OS Duration (mos.) | 13.2 |  | 18.0
95% CI (mos.) | (11.5, 15.2) |  | (15.5, 21.2)
Hazard Ratio (95% CI) |  | 0.66 (0.50, 0.87)

a Two patients on the FC arm who were FISH+ but IHC status unknown were excluded from the exploratory subgroup analyses.

b Five patients on the trastuzumab-containing arm who were FISH+, but IHC status unknown were excluded from the exploratory subgroup analyses.

c Includes 6 patients on chemotherapy arm, 10 patients on trastuzumab arm with FISH–, IHC3+ and 8 patients on chemotherapy arm, 8 patients on trastuzumab arm with FISH status unknown, IHC 3+.

16 HOW SUPPLIED/STORAGE AND HANDLING

Ogivri (trastuzumab-dkst) for injection 420 mg/vial is supplied in a multiple-dose vial as an off-white to pale yellow lyophilized sterile powder, under vacuum. Each carton contains one multiple-dose vial of Ogivri and one vial (20 mL) of Bacteriostatic Water for Injection (BWFI), USP, containing 1.1% benzyl alcohol as a preservative.

NDC 83257-004-12

Ogivri (trastuzumab-dkst) for injection 420 mg/vial is supplied in a multiple-dose vial as an off-white to pale yellow lyophilized sterile powder, under vacuum. Each carton contains one multiple-dose vial of Ogivri. No diluent is provided.

NDC 83257-003-01

Ogivri (trastuzumab-dkst) for injection 150 mg/vial is supplied in a single-dose vial as an off-white to pale yellow lyophilized sterile powder, under vacuum. Each carton contains one single-dose vial of Ogivri.

NDC 83257-001-11

Store Ogivri vials in the refrigerator at 2° to 8°C (36° to 46°F) until time of reconstitution.

17 PATIENT COUNSELING INFORMATION

Cardiomyopathy

- Advise patients to contact a health care professional immediately for any of the following: new onset or worsening shortness of breath, cough, swelling of the ankles/legs, swelling of the face, palpitations, weight gain of more than 5 pounds in 24 hours, dizziness or loss of consciousness [see Boxed Warning: Cardiomyopathy].

Embryo-Fetal Toxicity

- Advise pregnant women and females of reproductive potential that Ogivri exposure during pregnancy or within 7 months prior to conception can result in fetal harm. Advise female patients to contact their healthcare provider with a known or suspected pregnancy [see Use in Specific Populations (8.1)].
- Advise females of reproductive potential to use effective contraception during treatment and for 7 months following the last dose of Ogivri [see Use in Specific Populations (8.3)].

Ogivri® is a registered trademark of Biosimilars New Co. Ltd.; a Biocon Biologics Company.

Copyright © 2023 Biocon Biologics Inc. All rights reserved.

Manufactured by and for:

Biocon Biologics Inc.

245 Main st, 2nd floor

Cambridge, MA 02142, U.S.A.

U.S Licence No. 2324

KR/DRUGS/KTK/28D/07/2006

Revised: 11/2024

PRINCIPAL DISPLAY PANEL - 420 mg/vial with Diluent

NDC 83257-004-12

Rx only

Ogivri®
(trastuzumab-dkst)
For Injection
420 mg/vial

For intravenous infusion after reconstitution

No preservative

KEEP REFRIGERATED

Multiple-Dose
Vial

Contents: Each carton contains one 420 mg vial of Ogivri and one vial containing 20 mL of Bacteriostatic Water for Injection, USP (1.1% benzyl alcohol).

The content of each Ogivri® vial is 420 mg trastuzumab-dkst, D-sorbitol (322.6 mg), L-Histidine (6.0 mg), L-Histidine hydrochloride monohydrate (9.4 mg) and Polyethylene glycol 3350/Macrogol 3350 (94.1 mg). Hydrochloric acid or sodium hydroxide may be used to adjust the pH of the formulation buffer.

No U.S. standard of potency.

Bacteriostatic Water for Injection, USP is a sterile water containing 1.1% benzyl alcohol as an antimicrobial preservative packaged in a multi-use vial. The diluent is pH 4.5 to 7.

Store in refrigerator at 2° to 8°C (36° to 46°F) until time of reconstitution.

Reconstitution, Dosage, and Administration: Do not use if vacuum is not present. See prescribing information for dosage, preparation, and administration. Reconstitute with 20 mL Bacteriostatic Water for Injection (BWFI), USP (0.9% to 1.1% benzyl alcohol) to yield a multiple-dose solution containing 21 mg/mL trastuzumab-dkst that delivers 20 mL (420 mg trastuzumab-dkst). Do Not Shake. Store reconstituted solution in refrigerator at 2° to 8°C (36° to 46°F). Do not Freeze. Discard unused reconstituted solution after 28 days.

Do Not Freeze.

Do Not Shake Reconstituted Solution.

KEEP REFRIGERATED

Ogivri® and the Ogivri Logo are registered trademarks of Biosimilars New Co. Ltd.; a Biocon Biologics Company.

Copyright © 2023 Biocon Biologics Inc. All rights reservedy.

Manufactured by:
Biocon Biologics Inc.
245 Main st, 2nd floor
Cambridge, MA 02142, U.S.A.
U.S Licence No. 2324
Product of India

KR/DRUGS/KTK/28D/07/2006

PRINCIPAL DISPLAY PANEL -150 mg/vial

NDC 83257-001-11

Rx Only

Ogivri®
(trastuzumab-dkst)
For Injection
150 mg/vial

For intravenous infusion after reconstitution

No preservative

KEEP REFRIGERATED

Single-Dose Vial
Discard Unused
Portion

The content of each Ogivri® vial is 150 mg trastuzumab-dkst, D-sorbitol (115.2 mg), L-Histidine (2.16 mg), L-Histidine hydrochloride monohydrate (3.36 mg) and Polyethylene glycol 3350/Macrogol 3350 (33.6 mg). Hydrochloric acid or sodium hydroxide may be used to adjust the pH of the formulation buffer.

No U.S. standard of potency.

Usual dosage: See package insert for dosage, preparation, and administration information.

Storage: Refrigerate at 2° to 8°C (36° to 46°F) until time of reconstitution.

Reconstitute immediately before use.

Do Not Freeze. Do Not Shake After Reconstitution.

Ogivri® & the Ogivri Logo are registered trademarks of Biosimilars New Co. Ltd.; a Biocon Biologics Company.

Copyright © 2023 Biocon Biologics Inc.

All rights reserved.

Manufactured by:
Biocon Biologics Inc.
245 Main st, 2nd floor
Cambridge, MA 02142, U.S.A
U.S Licence No. 2324
Product of India

KR/DRUGS/KTK/28D/07/2006

PRINCIPAL DISPLAY PANEL -420 mg/vial

NDC 83257-003-01 Rx only

Ogivri®(trastuzumab-dkst)For Injection420 mg/vial

For intravenous infusion after reconstitution

No preservative

KEEP REFRIGERATED

Multiple-DoseVial

Contents: Each carton contains one 420 mg vial of Ogivri.

The content of each Ogivri® vial is 420 mg trastuzumab-dkst, D-sorbitol (322.6 mg), L-Histidine (6.0 mg), L-Histidine hydrochloride monohydrate (9.4 mg) and Polyethylene glycol 3350/Macrogol 3350 (94.1 mg). Hydrochloric acid or sodium hydroxide may be used to adjust the pH of the formulation buffer.

No U.S. standard of potency.

Store in refrigerator at 2° to 8°C (36° to 46°F) until time of reconstitution.

Reconstitution, Dosage, and Administration: Do not use if vacuum is not present. See prescribing information for dosage, preparation, and administration. Reconstitute with 20 mL Bacteriostatic Water for Injection (BWFI), USP (0.9% to 1.1% benzyl alcohol) to yield a multiple-dose solution containing 21 mg/mL trastuzumab-dkst that delivers 20 mL (420 mg trastuzumab-dkst). Do Not Shake. Store reconstituted solution in refrigerator at 2° to 8°C (36° to 46°F). Do not Freeze. Discard unused reconstituted solution after 28 days.

Do Not Freeze. Do Not Shake Reconstituted

Solution. KEEP REFRIGERATED

Ogivri® & the Ogivri Logo are registered trademarks of Biosimilars New Co. Ltd.; a Biocon Biologics Company.

Copyright © 2023 Biocon Biologics Inc.

All rights reserved.

Manufactured by:Biocon Biologics Inc.245 Main st, 2nd floor Cambridge, MA 02142, U.S.A.U.S Licence No. 2324 Product of India

KR/DRUGS/KTK/28D/07/2006